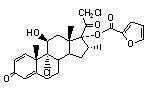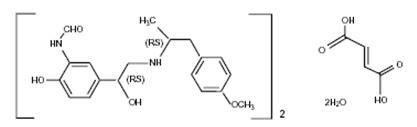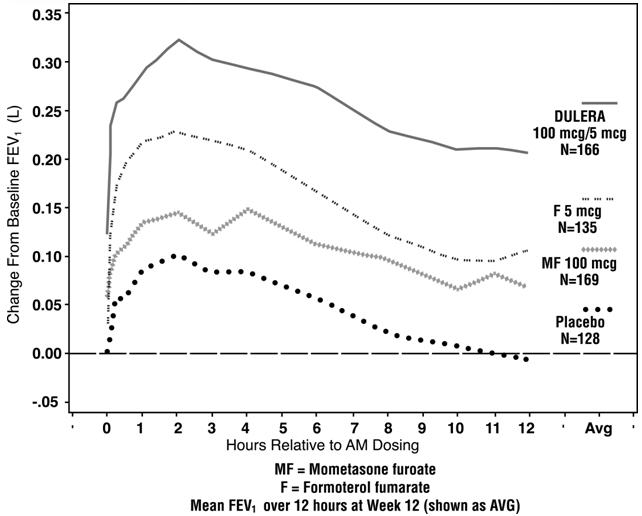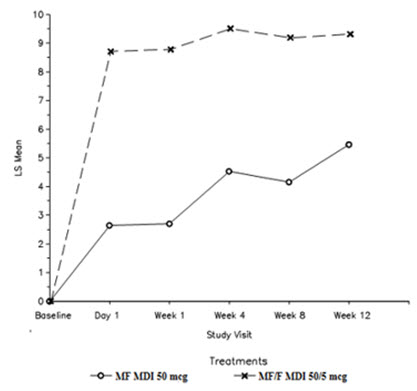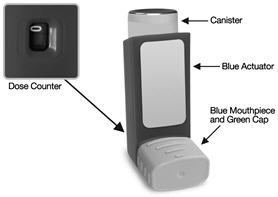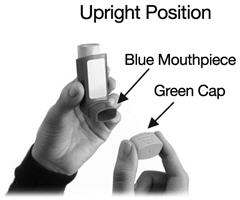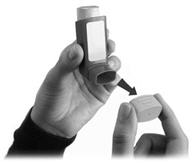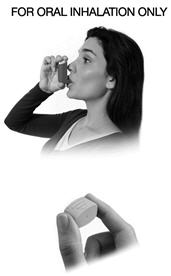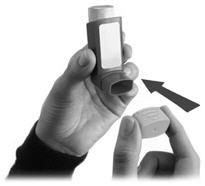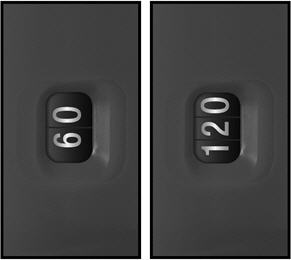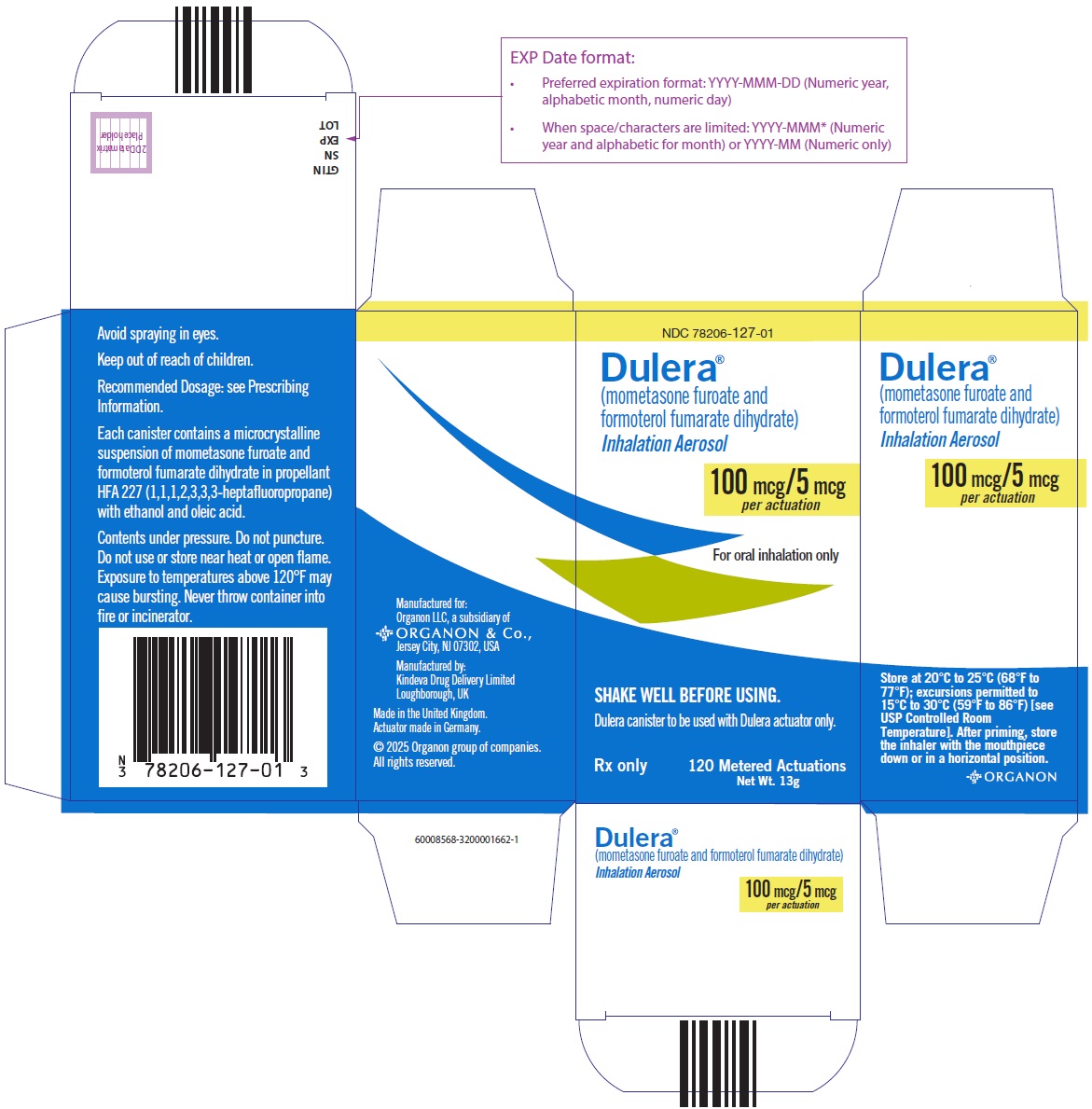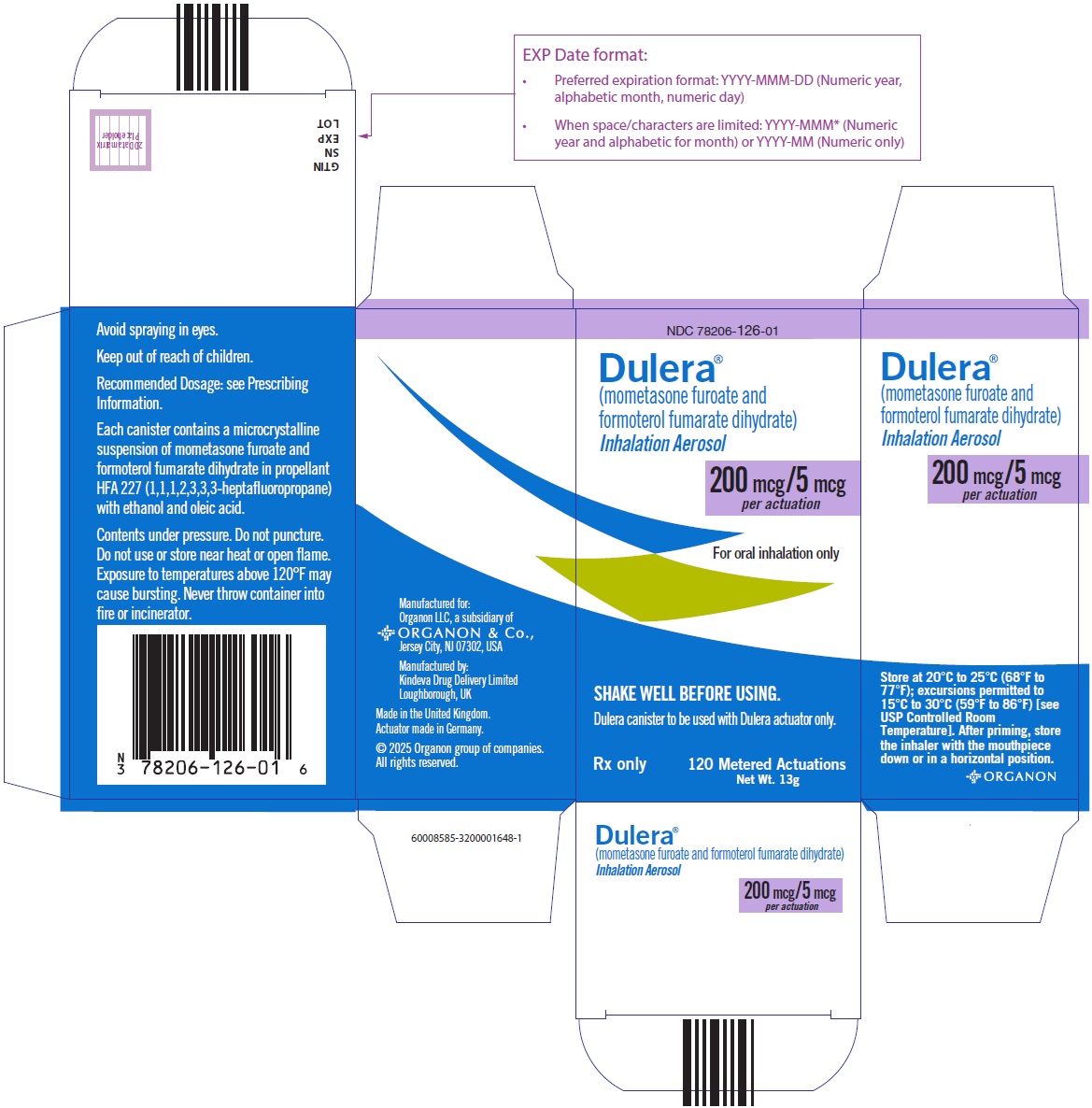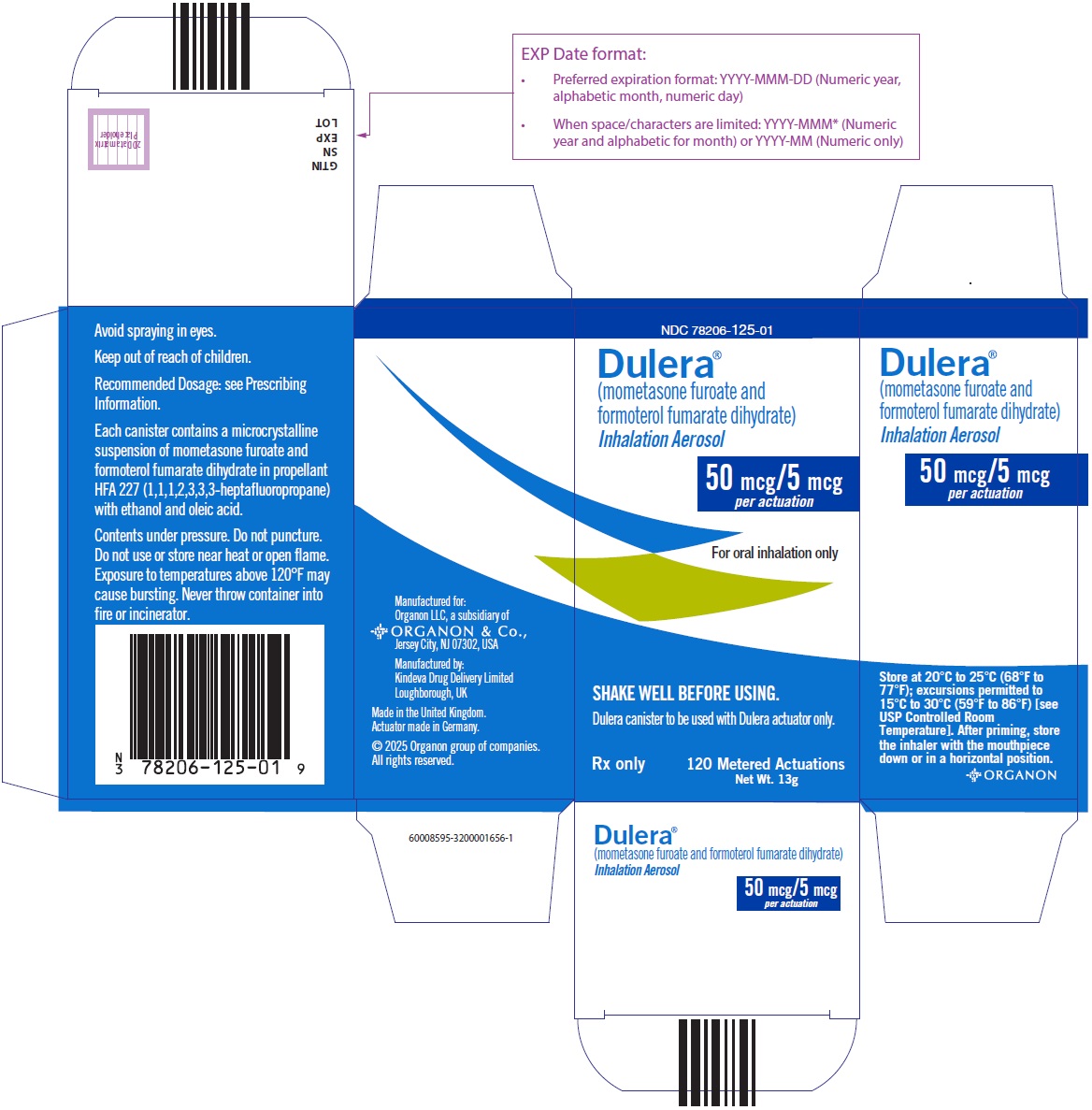 DRUG LABEL: Dulera
NDC: 78206-127 | Form: AEROSOL
Manufacturer: Organon LLC
Category: prescription | Type: HUMAN PRESCRIPTION DRUG LABEL
Date: 20260130

ACTIVE INGREDIENTS: mometasone furoate 100 ug/1 1; formoterol fumarate 5 ug/1 1
INACTIVE INGREDIENTS: alcohol; oleic acid

HIGHLIGHTS OF PRESCRIBING INFORMATION

These highlights do not include all the information needed to use DULERA safely and effectively. See full prescribing information for DULERA.
DULERA® (mometasone furoate and formoterol fumarate dihydrate) inhalation aerosol, for oral inhalation use
Initial U.S. Approval: 2010

1 INDICATIONS AND USAGE

DULERA is a combination product containing a corticosteroid and a long-acting beta2-adrenergic agonist (LABA) indicated for:

- Treatment of asthma in patients 5 years of age and older. (1.1)

Important Limitation of Use:

- Not indicated for the relief of acute bronchospasm. (1.1)

2 DOSAGE AND ADMINISTRATION

For oral inhalation only. (2.1)

Treatment of asthma in patients 12 years of age and older: 2 inhalations twice daily of DULERA 100 mcg/5 mcg or 200 mcg/5 mcg. Starting dosage is based on disease severity. (2.2)

Treatment of asthma in patients aged 5 to less than 12 years: 2 inhalations twice daily of DULERA 50 mcg/5 mcg. (2.2)

3 DOSAGE FORMS AND STRENGTHS

Inhalation aerosol containing a combination of mometasone furoate (50 mcg, 100 mcg, or 200 mcg) and formoterol fumarate dihydrate (5 mcg) per actuation. (3)

4 CONTRAINDICATIONS

- Primary treatment of status asthmaticus or acute episodes of asthma requiring intensive measures. (4.1)
- Hypersensitivity to any of the ingredients of DULERA. (4.2)

5 WARNINGS AND PRECAUTIONS

- LABA monotherapy increases the risk of serious asthma-related events. (5.1)
- Deterioration of disease and acute episodes: Do not initiate in acutely deteriorating asthma or to treat acute symptoms. (5.2)
- Use with additional long-acting beta2-agonist: Do not use in combination because of risk of overdose. (5.3)
- Localized infections: Candida albicans infection of the mouth and throat may occur. Monitor patients periodically for signs of adverse effects on the oral cavity. After dosing, advise patients to rinse their mouth with water and spit out contents without swallowing. (5.4)
- Immunosuppression: Potential worsening of existing tuberculosis, fungal, bacterial, viral, or parasitic infection; or ocular herpes simplex infections. More serious or even fatal course of chickenpox or measles can occur in susceptible patients. Use with caution in patients with these infections because of the potential for worsening of these infections. (5.5)
- Transferring patients from systemic corticosteroids: Risk of impaired adrenal function when transferring from oral steroids. Taper patients slowly from systemic corticosteroids if transferring to DULERA. (5.6)
- Hypercorticism and adrenal suppression: May occur with very high dosages or at the regular dosage in susceptible individuals. If such changes occur, discontinue DULERA slowly. (5.7)
- Strong cytochrome P450 3A4 inhibitors (e.g., ritonavir): Risk of increased systemic corticosteroid effects. Exercise caution when used with DULERA. (5.8)
- Paradoxical bronchospasm: Discontinue DULERA and institute alternative therapy if paradoxical bronchospasm occurs. (5.9)
- Patients with cardiovascular disorders: Use with caution because of beta-adrenergic stimulation. (5.11)
- Decreases in bone mineral density: Monitor patients with major risk factors for decreased bone mineral content. (5.12)
- Effects on growth: Monitor growth of pediatric patients. (5.13)
- Glaucoma and cataracts: Consider referral to an ophthalmologist in patients who develop ocular symptoms or use DULERA long term. (5.14)
- Coexisting conditions: Use with caution in patients with aneurysm, pheochromocytoma, convulsive disorders, thyrotoxicosis, diabetes mellitus, and ketoacidosis. (5.15)
- Hypokalemia and hyperglycemia: Be alert to hypokalemia and hyperglycemia. (5.16)

6 ADVERSE REACTIONS

Most common adverse reactions (reported in ≥3% in any treatment arm and greater than placebo) included:

- Nasopharyngitis, sinusitis and headache. (6.1)

To report SUSPECTED ADVERSE REACTIONS, contact Organon LLC, a subsidiary of Organon & Co., at 1-844-674-3200 or FDA at 1-800-FDA-1088 or www.fda.gov/medwatch.

7 DRUG INTERACTIONS

- Strong cytochrome P450 3A4 inhibitors (e.g., ritonavir): Use with caution. May cause increased systemic corticosteroid effects. (7.1)
- Adrenergic agents: Use with caution. Additional adrenergic drugs may potentiate sympathetic effects. (7.2)
- Xanthine derivatives and diuretics: Use with caution. May potentiate ECG changes and/or hypokalemia. (7.3, 7.4)
- MAO inhibitors, tricyclic antidepressants, macrolides, and drugs that prolong QTc interval: Use with extreme caution. May potentiate effect on the cardiovascular system. (7.5)
- Beta-blockers: Use with caution and only when medically necessary. May decrease effectiveness and produce severe bronchospasm. (7.6)
- Halogenated hydrocarbons: There is an elevated risk of arrhythmias in patients receiving concomitant anesthesia with halogenated hydrocarbons. (7.7)

8 USE IN SPECIFIC POPULATIONS

- Hepatic impairment: Monitor patients for signs of increased drug exposure. (8.6)

FULL PRESCRIBING INFORMATION

1 INDICATIONS AND USAGE

1.1 Treatment of Asthma

DULERA is indicated for the twice-daily treatment of asthma in patients 5 years of age and older. DULERA should be used for patients not adequately controlled on a long-term asthma-control medication such as an inhaled corticosteroid (ICS) or whose disease warrants initiation of treatment with both an ICS and long-acting beta2-adrenergic agonist (LABA).

Important Limitation of Use:

- DULERA is NOT indicated for the relief of acute bronchospasm.

2 DOSAGE AND ADMINISTRATION

2.1 Administration Information

Administer DULERA as two inhalations twice daily every day (morning and evening) by the orally inhaled route (see Patient Instructions for Use in the Patient Information leaflet). Do not use more than two inhalations twice daily of the prescribed strength of DULERA as some patients are more likely to experience adverse effects with higher doses of formoterol. If symptoms arise between doses, an inhaled short-acting beta2-agonist should be taken for immediate relief. Shake well prior to each inhalation. After each dose, advise patients to rinse their mouth with water and, without swallowing, spit out the contents to help reduce the risk of oropharyngeal candidiasis.

Remove the cap from the mouthpiece of the actuator before using DULERA.

Prime DULERA before using for the first time by releasing 4 test sprays into the air, away from the face, shaking well before each spray. In cases where the inhaler has not been used for more than 5 days, prime the inhaler again by releasing 4 test sprays into the air, away from the face, shaking well before each spray.

Only use the DULERA canister with the DULERA actuator. Do not use the DULERA actuator with any other inhalation drug product. Do not use actuators from other products with the DULERA canister.

2.2 Recommended Dosage

Administer DULERA as two inhalations twice daily every day (morning and evening) by the orally inhaled route. Shake well prior to each inhalation. Individual patients may experience a variable time to onset and degree of symptom relief. If symptoms arise between doses, use an inhaled short-acting beta2-agonist for immediate relief. Improvement in lung function following administration of DULERA can occur within 5 minutes of treatment, although the maximum benefit may not be achieved for 1 week or longer after beginning treatment.

Adult and Adolescent Patients Aged 12 Years and Older

For patients 12 years and older, the dosage is either 2 inhalations twice daily of DULERA 100 mcg/5 mcg or DULERA 200 mcg/5 mcg. When choosing the starting dosage strength of DULERA, consider the patients' disease severity, based on their previous asthma therapy, including the inhaled corticosteroid dosage, as well as the patients' current control of asthma symptoms and risk of future exacerbation. For patients who do not respond adequately after 2 weeks of therapy with two inhalations of DULERA 100 mcg/5 mcg twice daily (morning and evening), increasing the dosage to two inhalations of DULERA 200 mcg/5 mcg twice daily (morning and evening) may provide additional asthma control. The maximum recommended dosage is two inhalations of DULERA 200 mcg/5 mcg twice daily (maximum daily dosage 800 mcg/20 mcg).

After asthma stability has been achieved, it may be desirable to titrate to the lowest effective dosage to reduce the possibility of side effects.

If a previously effective dosage regimen of DULERA fails to provide adequate control of asthma, re-evaluate the therapeutic regimen and consider additional therapeutic options, e.g., replacing the current strength of DULERA with a higher strength, adding additional inhaled corticosteroid, or initiating oral corticosteroids.

Pediatric Patients Aged 5 to Less Than 12 Years

For patients aged 5 to less than 12 years, the dosage is 2 inhalations of DULERA 50 mcg/5 mcg twice daily. The maximum daily dosage is 200 mcg/20 mcg.

3 DOSAGE FORMS AND STRENGTHS

DULERA is a pressurized metered dose inhaler (MDI) that is available in 2 strengths (100 mcg/5 mcg or 200 mcg/5 mcg) for adult and adolescent patients aged 12 and older and 1 strength (50 mcg/5 mcg) for pediatric patients aged 5 to less than 12 years.

DULERA 50 mcg/5 mcg delivers 50 mcg of mometasone furoate and 5 mcg of formoterol fumarate dihydrate per actuation.

DULERA 100 mcg/5 mcg delivers 100 mcg of mometasone furoate and 5 mcg of formoterol fumarate dihydrate per actuation.

DULERA 200 mcg/5 mcg delivers 200 mcg of mometasone furoate and 5 mcg of formoterol fumarate dihydrate per actuation.

Each strength of DULERA is supplied with a blue colored actuator and green dust cap [see How Supplied/Storage and Handling (16.1)].

4 CONTRAINDICATIONS

4.1 Status Asthmaticus

DULERA is contraindicated in the primary treatment of status asthmaticus or other acute episodes of asthma where intensive measures are required.

4.2 Hypersensitivity

DULERA is contraindicated in patients with known hypersensitivity to mometasone furoate, formoterol fumarate, or any of the ingredients in DULERA [see Warnings and Precautions (5.10)].

5 WARNINGS AND PRECAUTIONS

5.1 Serious Asthma-Related Events – Hospitalizations, Intubations, and Death

Use of LABA as monotherapy (without ICS) for asthma is associated with an increased risk of asthma-related death [see Salmeterol Multicenter Asthma Research Trial (SMART)]. Available data from controlled clinical trials also suggest that use of LABA as monotherapy increases the risk of asthma-related hospitalization in pediatric and adolescent patients. These findings are considered a class effect of LABA monotherapy. When LABA are used in fixed-dose combination with ICS, data from large clinical trials do not show a significant increase in the risk of serious asthma-related events (hospitalizations, intubations, death) compared to ICS alone [see Serious Asthma-Related Events with ICS/LABA].

Serious Asthma-Related Events with ICS/LABA

Four large, 26-week, randomized, blinded, active-controlled clinical safety trials were conducted to evaluate the risk of serious asthma-related events when LABA were used in fixed-dose combination with ICS compared to ICS alone in patients with asthma. Three trials included adult and adolescent patients aged ≥12 years: one trial compared mometasone furoate/formoterol (DULERA) to mometasone furoate [see Clinical Studies (14.1)]; one trial compared fluticasone propionate/salmeterol inhalation powder to fluticasone propionate inhalation powder; and one trial compared budesonide/formoterol to budesonide. The fourth trial included pediatric patients 4 to 11 years of age and compared fluticasone propionate/salmeterol inhalation powder to fluticasone propionate inhalation powder. The primary safety endpoint for all four trials was serious asthma-related events (hospitalizations, intubations and death). A blinded adjudication committee determined whether events were asthma-related.

The three adult and adolescent trials were designed to rule out a risk margin of 2.0, and the pediatric trial was designed to rule out a risk of 2.7. Each individual trial met its pre-specified objective and demonstrated non-inferiority of ICS/LABA to ICS alone. A meta-analysis of the three adult and adolescent trials did not show a significant increase in risk of a serious asthma-related event with ICS/LABA fixed-dose combination compared with ICS alone (Table 1). These trials were not designed to rule out all risk for serious asthma-related events with ICS/LABA compared with ICS.

Table 1: Meta-Analysis of Serious Asthma-Related Events in Patients with Asthma Aged 12 Years and Older
 | ICS/LABA (N=17,537) [Randomized patients who had taken at least 1 dose of study drug. Planned treatment used for analysis.] | ICS (N=17,552) | ICS/LABA vs. ICS Hazard ratio (95% CI) [Estimated using a Cox proportional hazards model for time to first event with baseline hazards stratified by each of the 3 trials.]
Serious asthma-related event [Number of patients with events that occurred within 6 months after the first use of study drug or 7 days after the last date of study drug, whichever date was later. Patients can have one or more events, but only the first event was counted for analysis. A single, blinded, independent adjudication committee determined whether events were asthma-related.] | 116 | 105 | 1.10 (0.85, 1.44)
Asthma-related death | 2 | 0
Asthma-related intubation (endotracheal) | 1 | 2
Asthma-related hospitalization (≥24 hour stay) | 115 | 105
ICS = Inhaled Corticosteroid, LABA = Long-acting Beta2-adrenergic Agonist.

The pediatric safety trial included 6208 pediatric patients 4 to 11 years of age who received ICS/LABA (fluticasone propionate/salmeterol inhalation powder) or ICS (fluticasone propionate inhalation powder). In this trial, 27/3107 (0.9%) patients randomized to ICS/LABA and 21/3101 (0.7%) patients randomized to ICS experienced a serious asthma-related event. There were no asthma-related deaths or intubations. ICS/LABA did not show a significantly increased risk of a serious asthma-related event compared to ICS based on the pre-specified risk margin (2.7), with an estimated hazard ratio of time to first event of 1.29 (95% CI: 0.73, 2.27).

Salmeterol Multicenter Asthma Research Trial (SMART)

A 28-week, placebo-controlled U.S. trial that compared the safety of salmeterol with placebo, each added to usual asthma therapy, showed an increase in asthma-related deaths in patients receiving salmeterol (13/13,176 in patients treated with salmeterol vs. 3/13,179 in patients treated with placebo; relative risk: 4.37 [95% CI: 1.25, 15.34]). Use of background ICS was not required in SMART. The increased risk of asthma-related death is considered a class effect of LABA monotherapy.

Formoterol Monotherapy Studies

Clinical studies with formoterol used as monotherapy suggested a higher incidence of serious asthma exacerbation in patients who received formoterol than in those who received placebo. The sizes of these studies were not adequate to precisely quantify the difference in serious asthma exacerbations between treatment groups.

5.2 Deterioration of Disease and Acute Episodes

DULERA should not be initiated in patients during rapidly deteriorating or potentially life-threatening episodes of asthma. DULERA has not been studied in patients with acutely deteriorating asthma. The initiation of DULERA in this setting is not appropriate.

Increasing use of inhaled, short-acting beta2-agonists is a marker of deteriorating asthma. In this situation, the patient requires immediate re-evaluation with reassessment of the treatment regimen, giving special consideration to the possible need for replacing the current strength of DULERA with a higher strength, adding additional inhaled corticosteroid, or initiating systemic corticosteroids. Patients should not use more than 2 inhalations twice daily (morning and evening) of DULERA.

DULERA is not indicated for the relief of acute symptoms, i.e., as rescue therapy for the treatment of acute episodes of bronchospasm. An inhaled, short-acting beta2-agonist, not DULERA, should be used to relieve acute symptoms such as shortness of breath.

When beginning treatment with DULERA, patients who have been taking oral or inhaled, short-acting beta2-agonists on a regular basis (e.g., 4 times a day) should be instructed to discontinue the regular use of these drugs.

5.3 Excessive Use of DULERA and Use with Other Long-Acting Beta2-Agonists

As with other inhaled drugs containing beta2-adrenergic agents, DULERA should not be used more often than recommended, at higher doses than recommended, or in conjunction with other medications containing long-acting beta2-agonists, as an overdose may result. Clinically significant cardiovascular effects and fatalities have been reported in association with excessive use of inhaled sympathomimetic drugs. Patients using DULERA should not use an additional long-acting beta2-agonist (e.g., salmeterol, formoterol fumarate, arformoterol tartrate) for any reason, including prevention of exercise-induced bronchospasm (EIB) or the treatment of asthma.

5.4 Local Effects

In clinical trials, the development of localized infections of the mouth and pharynx with Candida albicans have occurred in patients treated with DULERA. If oropharyngeal candidiasis develops, treat with appropriate local or systemic (i.e., oral) antifungal therapy while remaining on treatment with DULERA therapy, but at times therapy with DULERA may need to be interrupted. To reduce the risk of oropharyngeal candidiasis, after dosing with DULERA, advise patients to rinse their mouth with water and spit out the contents without swallowing.

5.5 Immunosuppression

Persons who are using drugs that suppress the immune system are more susceptible to infections than healthy individuals.

Chickenpox and measles, for example, can have a more serious or even fatal course in susceptible children or adults using corticosteroids. In such children or adults who have not had these diseases or who are not properly immunized, particular care should be taken to avoid exposure. How the dose, route, and duration of corticosteroid administration affect the risk of developing a disseminated infection is not known. The contribution of the underlying disease and/or prior corticosteroid treatment to the risk is also not known. If exposed to chickenpox, prophylaxis with varicella zoster immune globulin (VZIG) or pooled intravenous immunoglobulin (IVIG) may be indicated. If exposed to measles, prophylaxis with pooled intramuscular immunoglobulin (IG) may be indicated. (See the respective package inserts for complete VZIG and IG prescribing information.) If chickenpox develops, treatment with antiviral agents may be considered.

DULERA should be used with caution, if at all, in patients with active or quiescent tuberculosis infection of the respiratory tract, untreated systemic fungal, bacterial, viral, or parasitic infections; or ocular herpes simplex.

5.6 Transferring Patients from Systemic Corticosteroid Therapy

Particular care is needed for patients who are transferred from systemically active corticosteroids to DULERA because deaths due to adrenal insufficiency have occurred in asthmatic patients during and after transfer from systemic corticosteroids to less systemically available inhaled corticosteroids. After withdrawal from systemic corticosteroids, a number of months are required for recovery of hypothalamic-pituitary-adrenal (HPA) function.

Patients who have been previously maintained on 20 mg or more per day of prednisone (or its equivalent) may be most susceptible, particularly when their systemic corticosteroids have been almost completely withdrawn. During this period of HPA suppression, patients may exhibit signs and symptoms of adrenal insufficiency when exposed to trauma, surgery, or infection (particularly gastroenteritis) or other conditions associated with severe electrolyte loss. Although DULERA may improve control of asthma symptoms during these episodes, in recommended doses it supplies less than normal physiological amounts of corticosteroid systemically and does NOT provide the mineralocorticoid activity necessary for coping with these emergencies.

During periods of stress or severe asthma attack, patients who have been withdrawn from systemic corticosteroids should be instructed to resume oral corticosteroids (in large doses) immediately and to contact their physicians for further instruction. These patients should also be instructed to carry a medical identification card indicating that they may need supplementary systemic corticosteroids during periods of stress or severe asthma attack.

Patients requiring systemic corticosteroids should be weaned slowly from systemic corticosteroid use after transferring to DULERA. Lung function (FEV1 or PEF), beta-agonist use, and asthma symptoms should be carefully monitored during withdrawal of systemic corticosteroids. In addition to monitoring asthma signs and symptoms, patients should be observed for signs and symptoms of adrenal insufficiency such as fatigue, lassitude, weakness, nausea and vomiting, and hypotension.

Transfer of patients from systemic corticosteroid therapy to DULERA may unmask allergic conditions previously suppressed by the systemic corticosteroid therapy, e.g., rhinitis, conjunctivitis, eczema, arthritis, and eosinophilic conditions.

During withdrawal from oral corticosteroids, some patients may experience symptoms of systemically active corticosteroid withdrawal, e.g., joint and/or muscular pain, lassitude, and depression, despite maintenance or even improvement of respiratory function.

5.7 Hypercorticism and Adrenal Suppression

Mometasone furoate, a component of DULERA, will often help control asthma symptoms with less suppression of HPA function than therapeutically equivalent oral doses of prednisone. Since mometasone furoate is absorbed into the circulation and can be systemically active at higher doses, the beneficial effects of DULERA in minimizing HPA dysfunction may be expected only when recommended dosages are not exceeded and individual patients are titrated to the lowest effective dose.

Because of the possibility of systemic absorption of inhaled corticosteroids, patients treated with DULERA should be observed carefully for any evidence of systemic corticosteroid effects. Particular care should be taken in observing patients postoperatively or during periods of stress for evidence of inadequate adrenal response.

It is possible that systemic corticosteroid effects such as hypercorticism and adrenal suppression (including adrenal crisis) may appear in a small number of patients, particularly when mometasone furoate is administered at higher than recommended doses over prolonged periods of time. If such effects occur, the dosage of DULERA should be reduced slowly, consistent with accepted procedures for reducing systemic corticosteroids and for management of asthma symptoms.

5.8 Drug Interactions with Strong Cytochrome P450 3A4 Inhibitors

Caution should be exercised when considering the coadministration of DULERA with ketoconazole, and other known strong CYP3A4 inhibitors (e.g., ritonavir, cobicistat-containing products, atazanavir, clarithromycin, indinavir, itraconazole, nefazodone, nelfinavir, saquinavir, telithromycin) because adverse effects related to increased systemic exposure to mometasone furoate may occur [see Drug Interactions (7.1) and Clinical Pharmacology (12.3)].

5.9 Paradoxical Bronchospasm and Upper Airway Symptoms

DULERA may produce inhalation induced bronchospasm with an immediate increase in wheezing after dosing that may be life-threatening. If inhalation induced bronchospasm occurs, it should be treated immediately with an inhaled, short-acting bronchodilator. DULERA should be discontinued immediately and alternative therapy instituted.

5.10 Immediate Hypersensitivity Reactions

Immediate hypersensitivity reactions may occur after administration of DULERA, as demonstrated by cases of urticaria, flushing, allergic dermatitis, and bronchospasm.

5.11 Cardiovascular and Central Nervous System Effects

Excessive beta-adrenergic stimulation has been associated with seizures, angina, hypertension or hypotension, tachycardia with rates up to 200 beats/min, arrhythmias, nervousness, headache, tremor, palpitation, nausea, dizziness, fatigue, malaise, and insomnia. Therefore, DULERA should be used with caution in patients with cardiovascular disorders, especially coronary insufficiency, cardiac arrhythmias, and hypertension.

Formoterol fumarate, a component of DULERA, can produce a clinically significant cardiovascular effect in some patients as measured by pulse rate, blood pressure, and/or symptoms. Although such effects are uncommon after administration of DULERA at recommended doses, if they occur, the drug may need to be discontinued. In addition, beta-agonists have been reported to produce ECG changes, such as flattening of the T wave, prolongation of the QTc interval, and ST segment depression. The clinical significance of these findings is unknown. Fatalities have been reported in association with excessive use of inhaled sympathomimetic drugs.

5.12 Reduction in Bone Mineral Density

Decreases in bone mineral density (BMD) have been observed with long-term administration of products containing inhaled corticosteroids, including mometasone furoate, one of the components of DULERA. The clinical significance of small changes in BMD with regard to long-term outcomes, such as fracture, is unknown. Patients with major risk factors for decreased bone mineral content, such as prolonged immobilization, family history of osteoporosis, or chronic use of drugs that can reduce bone mass (e.g., anticonvulsants and corticosteroids) should be monitored and treated with established standards of care.

In a 2-year double-blind study in 103 male and female asthma patients 18 to 50 years of age previously maintained on bronchodilator therapy (Baseline FEV1 85%–88% predicted), treatment with mometasone furoate dry powder inhaler (DPI) 200 mcg twice daily resulted in significant reductions in lumbar spine (LS) BMD at the end of the treatment period compared to placebo. The mean change from Baseline to Endpoint in the lumbar spine BMD was -0.015 (-1.43%) for the mometasone furoate group compared to 0.002 (0.25%) for the placebo group. In another 2-year double-blind study in 87 male and female asthma patients 18 to 50 years of age previously maintained on bronchodilator therapy (Baseline FEV1 82%–83% predicted), treatment with mometasone furoate 400 mcg twice daily demonstrated no statistically significant changes in lumbar spine BMD at the end of the treatment period compared to placebo. The mean change from Baseline to Endpoint in the lumbar spine BMD was -0.018 (-1.57%) for the mometasone furoate group compared to -0.006 (-0.43%) for the placebo group.

5.13 Effect on Growth

Orally inhaled corticosteroids, including DULERA, may cause a reduction in growth velocity when administered to pediatric patients. Monitor the growth of pediatric patients receiving DULERA routinely (e.g., via stadiometry). To minimize the systemic effects of orally inhaled corticosteroids, including DULERA, titrate each patient's dose to the lowest dosage that effectively controls his/her symptoms [see Use in Specific Populations (8.4)].

5.14 Glaucoma and Cataracts

Glaucoma, increased intraocular pressure, and cataracts have been reported following the use of long-term administration of inhaled corticosteroids, including mometasone furoate, a component of DULERA. Consider referral to an ophthalmologist in patients who develop ocular symptoms or use DULERA long term [see Adverse Reactions (6)].

5.15 Coexisting Conditions

DULERA, like other medications containing sympathomimetic amines, should be used with caution in patients with aneurysm, pheochromocytoma, convulsive disorders, or thyrotoxicosis; and in patients who are unusually responsive to sympathomimetic amines. Doses of the related beta2-agonist albuterol, when administered intravenously, have been reported to aggravate preexisting diabetes mellitus and ketoacidosis.

5.16 Hypokalemia and Hyperglycemia

Beta2-agonist medications may produce significant hypokalemia in some patients, possibly through intracellular shunting, which has the potential to produce adverse cardiovascular effects. The decrease in serum potassium is usually transient, not requiring supplementation. Clinically significant changes in blood glucose and/or serum potassium were seen infrequently during clinical studies with DULERA at recommended doses.

6 ADVERSE REACTIONS

LABA use may result in the following:

- Serious asthma-related events – hospitalizations, intubations, and death [see Warnings and Precautions (5.1)].
- Cardiovascular and central nervous system effects [see Warnings and Precautions (5.11)].

Systemic and local corticosteroid use may result in the following:

- Candida albicans infection [see Warnings and Precautions (5.4)]
- Immunosuppression [see Warnings and Precautions (5.5)]
- Hypercorticism and adrenal suppression [see Warnings and Precautions (5.7)]
- Growth effects in pediatrics [see Warnings and Precautions (5.13)]
- Glaucoma and cataracts [see Warnings and Precautions (5.14)]

Because clinical trials are conducted under widely varying conditions, adverse reaction rates observed in the clinical trials of a drug cannot be directly compared to rates in the clinical trials of another drug and may not reflect the rates observed in practice.

6.1 Clinical Trials Experience

Adult and Adolescent Patients Aged 12 Years and Older

The safety data described below is based on 3 clinical trials which randomized 1913 patients 12 years of age and older with asthma, including 679 patients exposed to DULERA for 12 to 26 weeks and 271 patients exposed for 1 year. DULERA was studied in two placebo- and active-controlled trials (n=781 and n=728, respectively) and in a long-term 52-week safety trial (n=404). In the 12 to 26-week clinical trials, the population was 12 to 84 years of age, 41% male and 59% female, 73% Caucasian, 27% non-Caucasian. Patients received two inhalations twice daily of DULERA (100 mcg/5 mcg or 200 mcg/5 mcg), mometasone furoate MDI (100 mcg or 200 mcg), formoterol MDI (5 mcg) or placebo. In the long-term 52-week active-comparator safety trial, the population was 12 years to 75 years of age with asthma, 37% male and 63% female, 47% Caucasian, 53% non-Caucasian and received two inhalations twice daily of DULERA 100 mcg/5 mcg or 200 mcg/5 mcg, or an active comparator.

The incidence of treatment emergent adverse events associated with DULERA in Table 2 below is based upon pooled data from 2 clinical trials 12 to 26 weeks in duration in patients 12 years and older treated with two inhalations twice daily of DULERA (100 mcg/5 mcg or 200 mcg/5 mcg), mometasone furoate MDI (100 mcg or 200 mcg), formoterol MDI (5mcg) or placebo.

Table 2: Treatment-Emergent Adverse Events in DULERA Groups Occurring at an Incidence of ≥3% and More Commonly than Placebo
Adverse Reactions | DULERA [All treatments were administered as two inhalations twice daily.] |  | Mometasone Furoate |  | Formoterol | Placebo
Adverse Reactions | 100 mcg/5 mcg n=424 n (%) | 200 mcg/5 mcg n=255 n (%) | 100 mcg n=192 n (%) | 200 mcg n=240 n (%) | 5 mcg n=202 n (%) | n=196 n (%)
Nasopharyngitis | 20 (4.7) | 12 (4.7) | 15 (7.8) | 13 (5.4) | 13 (6.4) | 7 (3.6)
Sinusitis | 14 (3.3) | 5 (2.0) | 6 (3.1) | 4 (1.7) | 7 (3.5) | 2 (1.0)
Headache | 19 (4.5) | 5 (2.0) | 10 (5.2) | 8 (3.3) | 6 (3.0) | 7 (3.6)
Average Duration of Exposure (days) | 116 | 81 | 165 | 79 | 131 | 138

Oral candidiasis has been reported in clinical trials at an incidence of 0.7% in patients using DULERA 100 mcg/5 mcg, 0.8% in patients using DULERA 200 mcg/5 mcg and 0.5% in the placebo group.

Long-Term Clinical Trial Experience

In a long-term safety trial in patients 12 years and older treated for 52 weeks with DULERA 100 mcg/5 mcg (n=141), DULERA 200 mcg/5 mcg (n=130) or an active comparator (n=133), safety outcomes in general were similar to those observed in the shorter 12 to 26 week controlled trials. No asthma-related deaths were observed. Dysphonia was observed at a higher frequency in the longer term treatment trial at a reported incidence of 7/141 (5%) patients receiving DULERA 100 mcg/5 mcg and 5/130 (3.8%) patients receiving DULERA 200 mcg/5 mcg. No clinically significant changes in blood chemistry, hematology, or ECG were observed.

Pediatric Patients Aged 5 to Less Than 12 Years

The safety data for pediatric patients aged 5 to less than 12 years are primarily based on a clinical trial of 24 weeks treatment duration with a 2-week safety follow-up. A total of 181 patients with asthma (92 male and 89 female) who were receiving any ICS/LABA therapy at trial entry were randomized to either DULERA 50 mcg/5 mcg (n=91) or mometasone furoate MDI 50 mcg (n=90), administered as 2 inhalations twice daily. The mean age was 9.1 years, 22.1% were between the ages of 5 to 7, and more than half (53.6%) of the population was non-Caucasian, with 38.7% of the total population reporting at least two races (i.e., multiracial). Common treatment-emergent adverse events that occurred in patients treated with DULERA with an incidence of ≥3% and more frequently than patients treated with mometasone furoate alone included influenza, upper respiratory tract infection, and headache.

Overall, the safety profile for pediatric patients is similar to that observed in patients aged 12 years and older.

6.2 Postmarketing Experience

The following adverse reactions have been reported during post-approval use of DULERA or post-approval use with inhaled mometasone furoate or inhaled formoterol fumarate. Because these reactions are reported voluntarily from a population of uncertain size, it is not always possible to reliably estimate their frequency or establish a causal relationship to drug exposure.

Cardiac disorders: angina pectoris, cardiac arrhythmias, e.g., atrial fibrillation, ventricular extrasystoles, tachyarrhythmia

Eye disorders: vision blurred [see Warnings and Precautions (5.14)]

Immune system disorders: immediate and delayed hypersensitivity reactions including anaphylactic reaction, angioedema, severe hypotension, rash, pruritus

Investigations: electrocardiogram QT prolonged, blood pressure increased (including hypertension)

Metabolism and nutrition disorders: hypokalemia, hyperglycemia

Respiratory, thoracic and mediastinal disorders: asthma aggravation, which may include cough, dyspnea, wheezing and bronchospasm

7 DRUG INTERACTIONS

In clinical trials, concurrent administration of DULERA and other drugs, such as short-acting beta2-agonist and intranasal corticosteroids have not resulted in an increased frequency of adverse drug reactions. No formal drug interaction studies have been performed with DULERA. The drug interactions of the combination are expected to reflect those of the individual components.

7.1 Inhibitors of Cytochrome P450 3A4

The main route of metabolism of corticosteroids, including mometasone furoate, a component of DULERA, is via cytochrome P450 (CYP) isoenzyme 3A4 (CYP3A4). After oral administration of ketoconazole, a strong inhibitor of CYP3A4, the mean plasma concentration of orally inhaled mometasone furoate increased. Concomitant administration of CYP3A4 inhibitors may inhibit the metabolism of, and increase the systemic exposure to, mometasone furoate and potentially increase the risk for systemic corticosteroid side effects. Caution should be exercised when considering the coadministration of DULERA with long-term ketoconazole and other known strong CYP3A4 inhibitors (e.g., ritonavir, cobicistat-containing products, atazanavir, clarithromycin, indinavir, itraconazole, nefazodone, nelfinavir, saquinavir, telithromycin) [see Warnings and Precautions (5.8) and Clinical Pharmacology (12.3)]. Consider the benefit of coadministration versus the potential risk of systemic corticosteroid effects, in which case patients should be monitored for systemic corticosteroid side effects.

7.2 Adrenergic Agents

If additional adrenergic drugs are to be administered by any route, they should be used with caution because the pharmacologically predictable sympathetic effects of formoterol, a component of DULERA, may be potentiated.

7.3 Xanthine Derivatives

Concomitant treatment with xanthine derivatives may potentiate any hypokalemic effect of formoterol, a component of DULERA.

7.4 Diuretics

Concomitant treatment with diuretics may potentiate the possible hypokalemic effect of adrenergic agonists. The ECG changes and/or hypokalemia that may result from the administration of non-potassium-sparing diuretics (such as loop or thiazide diuretics) can be acutely worsened by beta-agonists, especially when the recommended dose of the beta-agonist is exceeded. Although the clinical significance of these effects is not known, caution is advised in the coadministration of DULERA with non-potassium-sparing diuretics.

7.5 Monoamine Oxidase Inhibitors, Tricyclic Antidepressants, and Drugs Known to Prolong the QTc Interval

DULERA should be administered with caution to patients being treated with monoamine oxidase inhibitors, tricyclic antidepressants, macrolides, or drugs known to prolong the QTc interval or within 2 weeks of discontinuation of such agents, because the action of formoterol, a component of DULERA, on the cardiovascular system may be potentiated by these agents. Drugs that are known to prolong the QTc interval have an increased risk of ventricular arrhythmias.

7.6 Beta-Adrenergic Receptor Antagonists

Beta-adrenergic receptor antagonists (beta-blockers) and formoterol may inhibit the effect of each other when administered concurrently. Beta-blockers not only block the therapeutic effects of beta2-agonists, such as formoterol, a component of DULERA, but may produce severe bronchospasm in patients with asthma. Therefore, patients with asthma should not normally be treated with beta-blockers. However, under certain circumstances, e.g., as prophylaxis after myocardial infarction, there may be no acceptable alternatives to the use of beta-blockers in patients with asthma. In this setting, cardioselective beta-blockers could be considered, although they should be administered with caution.

7.7 Halogenated Hydrocarbons

There is an elevated risk of arrhythmias in patients receiving concomitant anesthesia with halogenated hydrocarbons.

8 USE IN SPECIFIC POPULATIONS

8.1 Pregnancy

Risk Summary

There are no randomized clinical studies of DULERA, mometasone furoate, or formoterol fumarate in pregnant women. There are clinical considerations with the use of DULERA in pregnant women [see Clinical Considerations]. Animal reproduction studies with DULERA are not available; however, studies are available with its individual components, mometasone furoate and formoterol fumarate. In animal reproduction studies, subcutaneous administration of mometasone furoate to pregnant mice, rats, or rabbits caused increased fetal malformations and decreased fetal survival and growth following administration of doses that produced exposures approximately 1/3 to 8 times the maximum recommended human dose (MRHD) on a mcg/m^2 or AUC basis [see Data]. However, experience with oral corticosteroids suggests that rodents are more prone to teratogenic effects from corticosteroid exposure than humans. In animal reproduction studies, oral administration of formoterol fumarate to pregnant rats and rabbits caused increased fetal malformations (rats and rabbits), decreased fetal weight (rats), and increased neonatal mortality (rats) following administration of doses that produced exposures approximately 1200 to 49,000 times the MRHD on a mg/m^2 or AUC basis [see Data]. These adverse effects generally occurred at large multiples of the MRHD when formoterol fumarate was administered by the oral route to achieve high systemic exposures. No effects were observed in a study with rats that received formoterol fumarate by the inhalation route at an exposure approximately 500 times the MRHD.

The estimated background risk of major birth defects and miscarriage for the indicated population is unknown. In the U.S. general population, the estimated risk of major birth defects and miscarriage in clinically recognized pregnancies is 2 to 4% and 15 to 20%, respectively.

Clinical Considerations

Disease-associated maternal and/or embryo/fetal risk

In women with poorly or moderately controlled asthma, there is an increased risk of several perinatal adverse outcomes such as preeclampsia in the mother and prematurity, low birth weight, and small for gestational age in the neonate. Pregnant women with asthma should be closely monitored and medication adjusted as necessary to maintain optimal asthma control.

Labor or delivery

There are no adequate and well-controlled human studies that have studied the effects of DULERA during labor and delivery. Because of the potential for beta-agonist interference with uterine contractility, use of DULERA during labor should be restricted to those patients in whom the benefits clearly outweigh the risk.

Data

Animal Data

Mometasone Furoate

In an embryofetal development study with pregnant mice dosed throughout the period of organogenesis, mometasone furoate produced cleft palate at an exposure approximately one-third of the MRHD (on a mcg/m^2 basis with maternal subcutaneous doses of 60 mcg/kg and above) and decreased fetal survival at an exposure approximately equivalent to the MRHD (on a mcg/m^2 basis with a maternal subcutaneous dose of 180 mcg/kg). No toxicity was observed with a dose that produced an exposure approximately one-tenth of the MRHD (on a mcg/m^2 basis with maternal topical dermal doses of 20 mcg/kg and above).

In an embryofetal development study with pregnant rats dosed throughout the period of organogenesis, mometasone furoate produced fetal umbilical hernia at exposures approximately 6 times the MRHD (on a mcg/m^2 basis with maternal topical dermal doses of 600 mcg/kg and above) and delays in fetal ossification at exposures approximately 3 times the MRHD (on a mcg/m^2 basis with maternal topical dermal doses of 300 mcg/kg and above).

In another reproductive toxicity study, pregnant rats were dosed with mometasone furoate throughout pregnancy or late in gestation. Treated animals had prolonged and difficult labor, fewer live births, lower birth weight, and reduced early pup survival at an exposure that was approximately 8 times the MRHD (on an area under the curve (AUC) basis with a maternal subcutaneous dose of 15 mcg/kg). There were no findings with an exposure approximately 4 times the MRHD (on an AUC basis with a maternal subcutaneous dose of 7.5 mcg/kg).

Embryofetal development studies were conducted with pregnant rabbits dosed with mometasone furoate by either the topical dermal route or oral route throughout the period of organogenesis. In the study using the topical dermal route, mometasone furoate caused multiple malformations in fetuses (e.g., flexed front paws, gallbladder agenesis, umbilical hernia, hydrocephaly) at an exposure approximately 3 times the MRHD (on a mcg/m^2 basis with maternal topical dermal doses of 150 mcg/kg and above). In the study using the oral route, mometasone furoate caused increased fetal resorptions and cleft palate and/or head malformations (hydrocephaly and domed head) at an exposure approximately 1/2 of the MRHD (on AUC basis with a maternal oral dose of 700 mcg/kg). At an exposure approximately 2 times the MRHD (on an AUC basis with a maternal oral dose of 2800 mcg/kg), most litters were aborted or resorbed. No effects were observed at an exposure approximately 1/10 of the MRHD (on an AUC basis with a maternal oral dose of 140 mcg/kg).

Formoterol Fumarate

In embryofetal development studies with pregnant rats and rabbits dosed throughout the period of organogenesis, formoterol fumarate did not cause malformations in either species. However, for pregnant rats dosed throughout organogenesis, formoterol fumarate caused delayed fetal ossification at an exposure approximately 80 times the MRHD (on a mcg/m^2 basis with maternal oral doses of 200 mcg/kg and higher) and decreased fetal weight at an exposure approximately 2400 times the MRHD (on a mcg/m^2 basis with maternal oral doses of 6000 mcg/kg and above). In a pre- and post-natal development study with rats dosed during the late stage of pregnancy, formoterol fumarate caused stillbirth and neonatal mortality at an exposure approximately 2400 times the MRHD (on a mcg/m^2 basis with maternal oral doses of 6000 mcg/kg and above). However, no effects were observed in this study at an exposure approximately 80 times the MRHD (on a mcg/m^2 basis with a maternal oral dose of 200 mcg/kg).

In embryofetal development studies, conducted by another testing laboratory, with pregnant rats and rabbits dosed throughout the period of organogenesis, formoterol fumarate was teratogenic in both species. Umbilical hernia, a malformation, was observed in rat fetuses at exposures approximately 1200 times the MRHD (on a mcg/m^2 basis with maternal oral doses of 3000 mcg/kg/day and above). Brachygnathia, a skeletal malformation, was observed in rat fetuses at an exposure approximately 6100 times the MRHD (on a mcg/m^2 basis with a maternal oral dose of 15,000 mcg/kg/day). In another study with rats, no teratogenic effects were observed with exposures up to approximately 500 times the MRHD (on a mcg/m^2 basis with a maternal inhalation dose of 1200 mcg/kg/day). Subcapsular cysts on the liver were observed in rabbit fetuses at an exposure approximately 49,000 times the MRHD (on a mcg/m^2 basis with a maternal oral dose of 60,000 mcg/kg/day). No teratogenic effects were observed with exposures up to approximately 3000 times the MRHD (on a mcg/m^2 basis with a maternal oral dose of 3500 mcg/kg).

8.2 Lactation

Risk Summary

There are no available data on the presence of DULERA, mometasone furoate, or formoterol fumarate in human milk, the effects on the breastfed child, or the effects on milk production. Other inhaled corticosteroids, similar to mometasone furoate, are present in human milk. Formoterol fumarate is present in rat milk; however, due to species specific differences in lactation physiology, animal lactation data may not reliably predict levels in human milk. The developmental and health benefits of breastfeeding should be considered along with the mother's clinical need for DULERA and any potential adverse effects on the breastfed infant from DULERA or from the underlying maternal condition.

8.4 Pediatric Use

The safety and effectiveness of DULERA have been established in patients 12 years of age and older in 3 clinical trials up to 52 weeks in duration. In the 3 clinical trials, 101 patients 12 to 17 years of age were treated with DULERA. Patients in this age-group demonstrated efficacy results similar to those observed in patients 18 years of age and older. There were no obvious differences in the type or frequency of adverse reactions reported in this age group compared to patients 18 years of age and older. Similar efficacy and safety results were observed in an additional 22 patients 12 to 17 years of age who were treated with DULERA in another clinical trial.

The safety and effectiveness of DULERA 50 mcg/5 mcg, two inhalations twice daily, have been established in patients with asthma aged 5 to less than 12 years in clinical trials up to 24 weeks of treatment duration. Patients in this age group demonstrated efficacy and safety results similar to those observed in patients aged 12 years and older who were treated with DULERA [see Adverse Reactions (6.1) and Clinical Studies (14.1)].

The safety and effectiveness of DULERA have not been established in children younger than 5 years of age.

Controlled clinical studies have shown that inhaled corticosteroids may cause a reduction in growth velocity in pediatric patients. In these studies, the mean reduction in growth velocity was approximately 1 cm per year (range 0.3 to 1.8 per year) and appears to depend upon dose and duration of exposure. This effect was observed in the absence of laboratory evidence of hypothalamic-pituitary-adrenal (HPA) axis suppression, suggesting that growth velocity is a more sensitive indicator of systemic corticosteroid exposure in pediatric patients than some commonly used tests of HPA axis function. The long-term effects of this reduction in growth velocity associated with orally inhaled corticosteroids, including the impact on final adult height, are unknown. The potential for "catch up" growth following discontinuation of treatment with orally inhaled corticosteroids has not been adequately studied.

The growth of children and adolescents receiving orally inhaled corticosteroids, including DULERA, should be monitored routinely (e.g., via stadiometry). If a child or adolescent on any corticosteroid appears to have growth suppression, the possibility that he/she is particularly sensitive to this effect should be considered. The potential growth effects of prolonged treatment should be weighed against clinical benefits obtained and the risks associated with alternative therapies. To minimize the systemic effects of orally inhaled corticosteroids, including DULERA, each patient should be titrated to his/her lowest effective dose [see Dosage and Administration (2.2)].

8.5 Geriatric Use

A total of 77 patients 65 years of age and older (11 of whom were 75 years and older) have been treated with DULERA in 3 clinical trials up to 52 weeks in duration. Similar efficacy and safety results were observed in an additional 28 patients 65 years of age and older who were treated with DULERA in another clinical trial. No overall differences in safety or effectiveness were observed between these patients and younger patients, but greater sensitivity of some older individuals cannot be ruled out. As with other products containing beta2-agonists, special caution should be observed when using DULERA in geriatric patients who have concomitant cardiovascular disease that could be adversely affected by beta2-agonists. Based on available data for DULERA or its active components, no adjustment of dosage of DULERA in geriatric patients is warranted.

8.6 Hepatic Impairment

Concentrations of mometasone furoate appear to increase with severity of hepatic impairment [see Clinical Pharmacology (12.3)].

10 OVERDOSAGE

10.1 Signs and Symptoms

DULERA: DULERA contains both mometasone furoate and formoterol fumarate; therefore, the risks associated with overdosage for the individual components described below apply to DULERA.

Mometasone Furoate: Chronic overdosage may result in signs/symptoms of hypercorticism [see Warnings and Precautions (5.7)]. Single oral doses up to 8000 mcg of mometasone furoate have been studied on adult subjects with no adverse reactions reported.

Formoterol Fumarate: The expected signs and symptoms with overdosage of formoterol are those of excessive beta-adrenergic stimulation and/or occurrence or exaggeration of any of the following signs and symptoms: angina, hypertension or hypotension, tachycardia, with rates up to 200 beats/min., arrhythmias, nervousness, headache, tremor, seizures, muscle cramps, dry mouth, palpitation, nausea, dizziness, fatigue, malaise, hypokalemia, hyperglycemia, and insomnia. Metabolic acidosis may also occur. Cardiac arrest and even death may be associated with an overdose of formoterol.

The minimum acute lethal inhalation dose of formoterol fumarate in rats is 156 mg/kg (approximately 63,000 times the MRHD on a mcg/m^2 basis). The median lethal oral doses in Chinese hamsters, rats, and mice provide even higher multiples of the MRHD.

10.2 Treatment

DULERA: Treatment of overdosage consists of discontinuation of DULERA together with institution of appropriate symptomatic and/or supportive therapy. The judicious use of a cardioselective beta-receptor blocker may be considered, bearing in mind that such medication can produce bronchospasm. There is insufficient evidence to determine if dialysis is beneficial for overdosage of DULERA. Cardiac monitoring is recommended in cases of overdosage.

11 DESCRIPTION

DULERA 50 mcg/5 mcg, DULERA 100 mcg/5 mcg, and DULERA 200 mcg/5 mcg are combinations of mometasone furoate and formoterol fumarate dihydrate for oral inhalation only.

One active component of DULERA is mometasone furoate, a corticosteroid having the chemical name 9,21-dichloro-11(Beta),17-dihydroxy-16 (alpha)-methylpregna-1,4-diene-3,20-dione 17-(2-furoate) with the following chemical structure:

Mometasone furoate is a white powder with an empirical formula of C27H30Cl2O6, and molecular weight 521.44. It is practically insoluble in water; slightly soluble in methanol, ethanol, and isopropanol; soluble in acetone.

One active component of DULERA is formoterol fumarate dihydrate, a racemate. Formoterol fumarate dihydrate is a selective beta2-adrenergic bronchodilator having the chemical name of (±)-2-hydroxy-5-[(1RS)-1-hydroxy-2-[[(1RS)-2-(4-methoxyphenyl)-1-methylethyl]-amino]ethyl]formanilide fumarate dihydrate with the following chemical structure:

Formoterol fumarate dihydrate has a molecular weight of 840.9, and its empirical formula is (C19H24N2O4)2•C4H4O4•2H2O. Formoterol fumarate dihydrate is a white to yellowish powder, which is freely soluble in glacial acetic acid, soluble in methanol, sparingly soluble in ethanol and isopropanol, slightly soluble in water, and practically insoluble in acetone, ethyl acetate, and diethyl ether.

DULERA 50 mcg/5 mcg, 100 mcg/5 mcg, and 200 mcg/5 mcg are each formulated as a hydrofluoroalkane (HFA-227; 1, 1, 1, 2, 3, 3, 3-heptafluoropropane) propelled pressurized metered dose inhaler containing sufficient amount of drug for 60 or 120 inhalations [see How Supplied/Storage and Handling (16)]. After priming, each actuation of the inhaler delivers 60, 115, or 225 mcg of mometasone furoate and 5.5 mcg of formoterol fumarate dihydrate in 69.6 mg of suspension from the valve and delivers 50, 100, or 200 mcg of mometasone furoate and 5 mcg of formoterol fumarate dihydrate from the actuator. The actual amount of drug delivered to the lung may depend on patient factors, such as the coordination between actuation of the device and inspiration through the delivery system. DULERA also contains anhydrous alcohol as a cosolvent and oleic acid as a surfactant.

DULERA should be primed before using for the first time by releasing 4 test sprays into the air, away from the face, shaking well before each spray. In cases where the inhaler has not been used for more than 5 days, prime the inhaler again by releasing 4 test sprays into the air, away from the face, shaking well before each spray.

12 CLINICAL PHARMACOLOGY

12.1 Mechanism of Action

DULERA: DULERA contains both mometasone furoate and formoterol fumarate; therefore, the mechanisms of actions described below for the individual components apply to DULERA. These drugs represent two different classes of medications (a synthetic corticosteroid and a selective long-acting beta2-adrenergic receptor agonist) that have different effects on clinical, physiological, and inflammatory indices of asthma.

Mometasone furoate: Mometasone furoate is a corticosteroid demonstrating potent anti-inflammatory activity. The precise mechanism of corticosteroid action on asthma is not known. Inflammation is an important component in the pathogenesis of asthma. Corticosteroids have been shown to have a wide range of inhibitory effects on multiple cell types (e.g., mast cells, eosinophils, neutrophils, macrophages, and lymphocytes) and mediators (e.g., histamine, eicosanoids, leukotrienes, and cytokines) involved in inflammation and in the asthmatic response. These anti-inflammatory actions of corticosteroids may contribute to their efficacy in asthma.

Mometasone furoate has been shown in vitro to exhibit a binding affinity for the human glucocorticoid receptor, which is approximately 12 times that of dexamethasone, 7 times that of triamcinolone acetonide, 5 times that of budesonide, and 1.5 times that of fluticasone. The clinical significance of these findings is unknown.

Formoterol fumarate: Formoterol fumarate is a long-acting selective beta2-adrenergic receptor agonist (beta2-agonist). Inhaled formoterol fumarate acts locally in the lung as a bronchodilator. In vitro studies have shown that formoterol has more than 200-fold greater agonist activity at beta2-receptors than at beta1-receptors. Although beta2-receptors are the predominant adrenergic receptors in bronchial smooth muscle and beta1-receptors are the predominant receptors in the heart, there are also beta2-receptors in the human heart comprising 10% to 50% of the total beta-adrenergic receptors. The precise function of these receptors has not been established, but they raise the possibility that even highly selective beta2-agonists may have cardiac effects.

The pharmacologic effects of beta2-adrenoceptor agonist drugs, including formoterol, are at least in part attributable to stimulation of intracellular adenyl cyclase, the enzyme that catalyzes the conversion of adenosine triphosphate (ATP) to cyclic-3', 5'-adenosine monophosphate (cyclic AMP). Increased cyclic AMP levels cause relaxation of bronchial smooth muscle and inhibition of release of mediators of immediate hypersensitivity from cells, especially from mast cells.

In vitro tests show that formoterol is an inhibitor of the release of mast cell mediators, such as histamine and leukotrienes, from the human lung. Formoterol also inhibits histamine-induced plasma albumin extravasation in anesthetized guinea pigs and inhibits allergen-induced eosinophil influx in dogs with airway hyper-responsiveness. The relevance of these in vitro and animal findings to humans is unknown.

12.2 Pharmacodynamics

DULERA:

Adult and Adolescent Patients Aged 12 Years and Older

Cardiovascular Effects:

In a single-dose, double-blind placebo-controlled crossover trial in 25 adult patients with asthma, single-dose treatment of 10 mcg formoterol fumarate in combination with 400 mcg of mometasone furoate delivered via DULERA 200 mcg/5 mcg were compared to formoterol fumarate 10 mcg MDI, formoterol fumarate 12 mcg dry powder inhaler (DPI; nominal dose of formoterol fumarate delivered 10 mcg), or placebo. The degree of bronchodilation at 12 hours after dosing with DULERA was similar to formoterol fumarate delivered alone via MDI or DPI.

ECGs and blood samples for glucose and potassium were obtained prior to dosing and post dose. No downward trend in serum potassium was observed and values were within the normal range and appeared to be similar across all treatments over the 12 hour period. Mean blood glucose appeared similar across all groups for each time point. There was no evidence of significant hypokalemia or hyperglycemia in response to formoterol treatment.

No relevant changes in heart rate or changes in ECG data were observed with DULERA in the trial. No patients had a QTcB (QTc corrected by Bazett's formula) ≥500 msec during treatment.

In a single-dose crossover trial involving 24 adult healthy subjects, single dose of formoterol fumarate 10, 20, or 40 mcg in combination with 400 mcg of mometasone furoate delivered via DULERA were evaluated for safety (ECG, blood potassium and glucose changes). ECGs and blood samples for glucose and potassium were obtained at baseline and post dose. Decrease in mean serum potassium was similar across all three treatment groups (approximately 0.3 mmol/L) and values were within the normal range. No clinically significant increases in mean blood glucose values or heart rate were observed. No subjects had a QTcB >500 msec during treatment.

Three active- and placebo-controlled trials (study duration ranging from 12, 26, and 52 weeks) evaluated 1913 patients 12 years of age and older with asthma. No clinically meaningful changes were observed in potassium and glucose values, vital signs, or ECG parameters in patients receiving DULERA.

Pediatric Patients: Among 91 children with asthma aged 5 to less than 12 years treated with DULERA for up to 24 weeks, there were no notable changes from baseline in heart rate or blood pressure. There were no reports of hypokalemia or hypoglycemia.

HPA Axis Effects: Adults

The effects of inhaled mometasone furoate administered via DULERA on adrenal function were evaluated in two clinical trials in patients with asthma. HPA-axis function was assessed by 24-hour plasma cortisol AUC. Although both these trials have open-label design and contain small number of patients per treatment arm, results from these trials taken together demonstrated suppression of 24-hour plasma cortisol AUC for DULERA 200 mcg/5 mcg compared to placebo consistent with the known systemic effects of inhaled corticosteroid.

In a 42-day, open-label, placebo and active-controlled study 60 patients with asthma 18 years of age and older were randomized to receive two inhalations twice daily of 1 of the following treatments: DULERA 100 mcg/5 mcg, DULERA 200 mcg/5 mcg, fluticasone propionate/salmeterol xinafoate 230 mcg/21 mcg, or placebo. At Day 42, the mean change from baseline plasma cortisol AUC(0-24 hr) was 8%, 22% and 34% lower compared to placebo for the DULERA 100 mcg/5 mcg (n=13), DULERA 200 mcg/5 mcg (n=15) and fluticasone propionate/salmeterol xinafoate 230 mcg/21 mcg (n=16) treatment groups, respectively.

In a 52-week, open-label safety study, primary analysis of the plasma cortisol 24-hour AUC was performed on 57 patients with asthma who received 2 inhalations twice daily of DULERA 100 mcg/5 mcg, DULERA 200 mcg/5 mcg, fluticasone propionate/salmeterol xinafoate 125/25 mcg, or fluticasone propionate/salmeterol xinafoate 250/25 mcg. At Week 52, the mean plasma cortisol AUC(0-24 hr) was 2.2%, 29.6%, 16.7%, and 32.2% lower from baseline for the DULERA 100 mcg/5 mcg (n=18), DULERA 200 mcg/5 mcg (n=20), fluticasone propionate/salmeterol xinafoate 125/25 mcg (n=8), and fluticasone propionate/salmeterol xinafoate 250/25 mcg (n=11) treatment groups, respectively.

Other Mometasone Products:

Systemic effects of inhaled corticosteroids are related to systemic exposure. Pharmacokinetic data have demonstrated that, in adults, systemic exposure to mometasone furoate administered as DULERA is the same or lower than that of equivalent doses of inhaled mometasone furoate administered via DPI [see Clinical Pharmacology (12.3)]. Based upon the pharmacokinetic data, the systemic effects (e.g., HPA-axis suppression and growth retardation) of mometasone furoate delivered from DULERA in adult and pediatric patients would be expected to be no greater than what is reported for inhaled mometasone furoate when administered at comparable doses via DPI [see Use in Specific Populations (8.4)].

HPA Axis Effects: Adults

The potential effect of mometasone furoate via a dry powder inhaler (DPI) on the HPA axis was assessed in a 29-day study. A total of 64 adult patients with mild to moderate asthma were randomized to one of 4 treatment groups: mometasone furoate DPI 440 mcg twice daily, mometasone furoate DPI 880 mcg twice daily, oral prednisone 10 mg once daily, or placebo. The 30-minute post-cosyntropin stimulation serum cortisol concentration on Day 29 was 23.2 mcg/dl for the mometasone furoate DPI 440 mcg twice daily group and 20.8 mcg/dl for the mometasone furoate DPI 880 mcg twice daily group, compared to 14.5 mcg/dl for the oral prednisone 10 mg group and 25 mcg/dl for the placebo group. The difference between mometasone furoate DPI 880 mcg twice daily (twice the maximum recommended dose) and placebo was statistically significant.

HPA Axis Effect: Pediatrics

The potential effect of mometasone furoate via a DPI on the HPA axis was assessed in 50 children aged 6 to 11 years in a 29-day, randomized, double-blind, placebo-controlled, parallel-group clinical trial. In this study, the mean difference from placebo in plasma cortisol AUC(0-12hr) for DPI 110 mcg twice daily was 3.4 mcg∙hr/dL (95% CI: -14.0, 20.7) and for 220 mcg twice daily was -16.0 mcg∙hr/dL (95% CI: -33.9, 1.9). The mean difference from placebo in plasma cortisol AUC(0-12hr) for the 440 mcg twice daily group (eight times the currently recommended mometasone furoate dose via a DPI in children ages 4-11) was -17.9 mcg∙hr/dL (95% CI: -35.8, 0.0). The mean differences in urinary-free cortisol changes from baseline compared to placebo were 3.1 mcg/day (95% CI: -3.3, 9.6), 3.3 mcg/day (95% CI: -3.0, 9.7), and -2.0 mcg/day (95% CI: -8.6, 4.6) for the groups treated with 110 mcg twice daily, 220 mcg twice daily, and 440 mcg twice daily, respectively.

12.3 Pharmacokinetics

Absorption

Mometasone furoate:

Adult Healthy Subjects: The systemic exposures to mometasone furoate from DULERA versus mometasone furoate delivered via DPI were compared. Following oral inhalation of single and multiple doses of the DULERA, mometasone furoate was absorbed in healthy subjects with median Tmax values ranging from 0.50 to 4 hours. Following single-dose administration of higher than recommended dose of DULERA (4 inhalations of DULERA 200 mcg/5 mcg) in healthy subjects, the arithmetic mean (CV%) Cmax and AUC(0-12 hr) values for MF were 67.8 (49) pg/mL and 650 (51) pg∙hr/mL, respectively while the corresponding estimates following 5 days of BID dosing of DULERA 800 mcg/20 mcg were 241 (36) pg/mL and 2200 (35) pg∙hr/mL. Exposure to mometasone furoate increased with increasing inhaled dose of DULERA 100 mcg/5 mcg to 200 mcg/5 mcg. Studies using oral dosing of labeled and unlabeled drug have demonstrated that the oral systemic bioavailability of mometasone furoate is negligible (<1%).

The above study demonstrated that the systemic exposure to mometasone furoate (based on AUC) was approximately 52% and 25% lower on Day 1 and Day 5, respectively, following DULERA administration compared to mometasone furoate via a DPI.

Adult Asthma Patients: Following oral inhalation of single and multiple doses of the DULERA, mometasone furoate was absorbed in asthma patients with median Tmax values ranging from 1 to 2 hours. Following single-dose administration of DULERA 400 mcg/10 mcg, the arithmetic mean (CV%) Cmax and AUC(0-12 hr) values for MF were 20 (88) pg/mL and 170 (94) pg∙hr/mL, respectively while the corresponding estimates following BID dosing of DULERA 400 mcg/10 mcg at steady-state were 60 (36) pg/mL and 577 (40) pg∙hr/mL.

Formoterol fumarate:

Adult Healthy Subjects: When DULERA was administered to healthy subjects, formoterol was absorbed with median Tmax values ranging from 0.167 to 0.5 hour. In a single-dose study with DULERA 400 mcg/10 mcg in healthy subjects, arithmetic mean (CV%) Cmax and AUC for formoterol were 15 (50) pmol/L and 81 (51) pmol*h/L, respectively. Over the dose range of 10 to 40 mcg for formoterol from DULERA, the exposure to formoterol was dose proportional.

Adult Asthma Patients: When DULERA was administered to patients with asthma, formoterol was absorbed with median Tmax values ranging from 0.58 to 1.97 hours. In a single-dose study with DULERA 400 mcg/10 mcg in patients with asthma, arithmetic mean (CV%) Cmax and AUC(0-12 hr) for formoterol were 22 (29) pmol/L and 125 (42) pmol*h/L, respectively. Following multiple-dose administration of DULERA 400 mcg/10 mcg, the steady-state arithmetic mean (CV%) Cmax and AUC(0-12 hr) for formoterol were 41 (59) pmol/L and 226 (54) pmol*hr/L.

Distribution

Mometasone furoate: Based on the study employing a 1000 mcg inhaled dose of tritiated mometasone furoate inhalation powder in adult subjects, no appreciable accumulation of mometasone furoate in the red blood cells was found. Following an intravenous 400 mcg dose of mometasone furoate, the plasma concentrations showed a biphasic decline, with a mean steady-state volume of distribution of 152 liters. The in vitro protein binding for mometasone furoate was reported to be 98% to 99% (in a concentration range of 5 to 500 ng/mL).

Formoterol fumarate: The binding of formoterol to human plasma proteins in vitro was 61% to 64% at concentrations from 0.1 to 100 ng/mL. Binding to human serum albumin in vitro was 31% to 38% over a range of 5 to 500 ng/mL. The concentrations of formoterol used to assess the plasma protein binding were higher than those achieved in plasma following inhalation of a single 120 mcg dose.

Metabolism

Mometasone furoate: Studies have shown that mometasone furoate is primarily and extensively metabolized in the liver of all species investigated and undergoes extensive metabolism to multiple metabolites. In-vitro studies have confirmed the primary role of human liver cytochrome P-450 3A4 (CYP3A4) in the metabolism of this compound, however, no major metabolites were identified. Human liver CYP3A4 metabolizes mometasone furoate to 6-beta hydroxy mometasone furoate.

Formoterol fumarate: Formoterol is metabolized primarily by direct glucuronidation at either the phenolic or aliphatic hydroxyl group and O-demethylation followed by glucuronide conjugation at either phenolic hydroxyl groups. Minor pathways involve sulfate conjugation of formoterol and deformylation followed by sulfate conjugation. The most prominent pathway involves direct conjugation at the phenolic hydroxyl group. The second major pathway involves O-demethylation followed by conjugation at the phenolic 2'-hydroxyl group. Four cytochrome P450 isozymes (CYP2D6, CYP2C19, CYP2C9 and CYP2A6) are involved in the O-demethylation of formoterol. Formoterol did not inhibit CYP450 enzymes at therapeutically relevant concentrations. Some patients may be deficient in CYP2D6 or 2C19 or both. Whether a deficiency in one or both of these isozymes results in elevated systemic exposure to formoterol or systemic adverse effects has not been adequately explored.

Excretion

Mometasone furoate: Following an intravenous dosing, the terminal half-life was reported to be about 5 hours. Following the inhaled dose of tritiated 1000 mcg mometasone furoate, the radioactivity is excreted mainly in the feces (a mean of 74%), and to a small extent in the urine (a mean of 8%) up to 7 days. No radioactivity was associated with unchanged mometasone furoate in the urine. Absorbed mometasone furoate is cleared from plasma at a rate of approximately 12.5 mL/min/kg, independent of dose. The effective t½ for mometasone furoate following inhalation with DULERA was 25 hours in adult healthy subjects and in adult patients with asthma.

Formoterol fumarate: Following oral administration of 80 mcg of radiolabeled formoterol fumarate to 2 healthy subjects, 59% to 62% of the radioactivity was eliminated in the urine and 32% to 34% in the feces over a period of 104 hours. In an oral inhalation study with DULERA, renal clearance of formoterol from the blood was 217 mL/min. In single-dose studies, the mean t½ values for formoterol in plasma were 9.1 hours and 10.8 hours from the urinary excretion data. The accumulation of formoterol in plasma after multiple dose administration was consistent with the increase expected with a drug having a terminal t½ of 9 to 11 hour.

Following single inhaled doses ranging from 10 to 40 mcg to adult healthy subjects from the MF/F MDI, 6.2% to 6.8% of the formoterol dose was excreted in urine unchanged. The (R,R) and (S,S)-enantiomers accounted, respectively, for 37% and 63% of the formoterol recovered in urine. From urinary excretion rates measured in healthy subjects, the mean terminal elimination half-lives for the (R,R)- and (S,S)-enantiomers were determined to be 13 and 9.5 hours, respectively. The relative proportion of the two enantiomers remained constant over the dose range studied.

Special Populations

Hepatic/Renal Impairment: There are no data regarding the specific use of DULERA in patients with hepatic or renal impairment.

A study evaluating the administration of a single inhaled dose of 400 mcg mometasone furoate by a dry powder inhaler to adult patients with mild (n=4), moderate (n=4), and severe (n=4) hepatic impairment resulted in only 1 or 2 patients in each group having detectable peak plasma concentrations of mometasone furoate (ranging from 50–105 pcg/mL). The observed peak plasma concentrations appear to increase with severity of hepatic impairment; however, the numbers of detectable levels were few.

Gender and Race: Specific studies to examine the effects of gender and race on the pharmacokinetics of DULERA have not been specifically studied.

Geriatrics: The pharmacokinetics of DULERA have not been specifically studied in the elderly population.

Drug-Drug Interactions

A single-dose crossover study was conducted to compare the pharmacokinetics of 4 inhalations of the following: mometasone furoate MDI, formoterol MDI, DULERA (mometasone furoate/formoterol fumarate MDI), and mometasone furoate MDI plus formoterol fumarate MDI administered concurrently. The results of the study indicated that there was no evidence of a pharmacokinetic interaction between the two components of DULERA.

Inhibitors of Cytochrome P450 Enzymes: Ketoconazole: In a drug interaction study, an inhaled dose of mometasone furoate 400 mcg delivered by a dry powder inhaler was given to 24 adult healthy subjects twice daily for 9 days and ketoconazole 200 mg (as well as placebo) were given twice daily concomitantly on Days 4 to 9. Mometasone furoate plasma concentrations were <150 pcg/mL on Day 3 prior to coadministration of ketoconazole or placebo. Following concomitant administration of ketoconazole, 4 out of 12 subjects in the ketoconazole treatment group (n=12) had peak plasma concentrations of mometasone furoate >200 pcg/mL on Day 9 (211–324 pcg/mL). Mometasone furoate plasma levels appeared to increase and plasma cortisol levels appeared to decrease upon concomitant administration of ketoconazole.

Specific drug-drug interaction studies with formoterol have not been performed.

13 NONCLINICAL TOXICOLOGY

13.1 Carcinogenesis, Mutagenesis, Impairment of Fertility

Mometasone furoate: In a 2-year carcinogenicity study in Sprague Dawley® rats, mometasone furoate demonstrated no statistically significant increase in the incidence of tumors at inhalation doses up to 67 mcg/kg (approximately 14 times the MRHD on an AUC basis). In a 19-month carcinogenicity study in Swiss CD-1 mice, mometasone furoate demonstrated no statistically significant increase in the incidence of tumors at inhalation doses up to 160 mcg/kg (approximately 9 times the MRHD on an AUC basis).

Mometasone furoate increased chromosomal aberrations in an in vitro Chinese hamster ovary cell assay, but did not have this effect in an in vitro Chinese hamster lung cell assay. Mometasone furoate was not mutagenic in the Ames test or mouse lymphoma assay, and was not clastogenic in an in vivo mouse micronucleus assay, a rat bone marrow chromosomal aberration assay, or a mouse male germ-cell chromosomal aberration assay. Mometasone furoate also did not induce unscheduled DNA synthesis in vivo in rat hepatocytes.

In reproductive studies in rats, impairment of fertility was not produced by subcutaneous doses up to 15 mcg/kg (approximately 8 times the MRHD on an AUC basis).

Formoterol fumarate: The carcinogenic potential of formoterol fumarate has been evaluated in 2-year drinking water and dietary studies in both rats and mice. In rats, the incidence of ovarian leiomyomas was increased at doses of 15 mg/kg and above in the drinking water study and at 20 mg/kg in the dietary study, but not at dietary doses up to 5 mg/kg (AUC exposure approximately 265 times human exposure at the MRHD). In the dietary study, the incidence of benign ovarian theca-cell tumors was increased at doses of 0.5 mg/kg and above (AUC exposure at the low dose of 0.5 mg/kg was approximately 27 times human exposure at the MRHD). This finding was not observed in the drinking water study, nor was it seen in mice (see below).

In mice, the incidence of adrenal subcapsular adenomas and carcinomas was increased in males at doses of 69 mg/kg and above in the drinking water study, but not at doses up to 50 mg/kg (AUC exposure approximately 350 times human exposure at the MRHD) in the dietary study. The incidence of hepatocarcinomas was increased in the dietary study at doses of 20 and 50 mg/kg in females and 50 mg/kg in males, but not at doses up to 5 mg/kg in either males or females (AUC exposure approximately 35 times human exposure at the MRHD). Also in the dietary study, the incidence of uterine leiomyomas and leiomyosarcomas was increased at doses of 2 mg/kg and above (AUC exposure at the low dose of 2 mg/kg was approximately 14 times human exposure at the MRHD). Increases in leiomyomas of the rodent female genital tract have been similarly demonstrated with other beta-agonist drugs.

Formoterol fumarate was not mutagenic or clastogenic in the following tests: mutagenicity tests in bacterial and mammalian cells, chromosomal analyses in mammalian cells, unscheduled DNA synthesis repair tests in rat hepatocytes and human fibroblasts, transformation assay in mammalian fibroblasts and micronucleus tests in mice and rats.

Reproduction studies in rats revealed no impairment of fertility at oral doses up to 3 mg/kg (approximately 1200 times the MRHD on a mcg/m^2 basis).

13.2 Animal Toxicology and/or Pharmacology

Animal Pharmacology

Formoterol fumarate: Studies in laboratory animals (minipigs, rodents, and dogs) have demonstrated the occurrence of cardiac arrhythmias and sudden death (with histologic evidence of myocardial necrosis) when beta-agonists and methylxanthines are administered concurrently. The clinical significance of these findings is unknown.

14 CLINICAL STUDIES

14.1 Asthma

Adult and Adolescent Patients Aged 12 Years of Age and Older

The safety and efficacy of DULERA were demonstrated in two randomized, double-blind, parallel group, multicenter clinical trials of 12 to 26 weeks in duration involving 1509 patients 12 years of age and older with persistent asthma uncontrolled on medium or high dose inhaled corticosteroids (baseline FEV1 means of 66% to 73% of predicted normal). These studies included a 2 to 3-week run-in period with mometasone furoate to establish a certain level of asthma control. One clinical trial compared DULERA to placebo and the individual components, mometasone furoate and formoterol (Trial 1) and one clinical trial compared two different strengths of DULERA to mometasone furoate alone (Trial 2).

Trial 1: Clinical Trial with DULERA 100 mcg/5 mcg

This 26-week, placebo-controlled trial (NCT00383240) evaluated 781 patients 12 years of age and older comparing DULERA 100 mcg/5 mcg (n=191 patients), mometasone furoate 100 mcg (n=192 patients), formoterol fumarate 5 mcg (n=202 patients) and placebo (n=196 patients); each administered as 2 inhalations twice daily by metered dose inhalation aerosols. All other maintenance therapies were discontinued. This study included a 2 to 3-week run-in period with mometasone furoate 100 mcg, 2 inhalations twice daily. This trial included patients ranging from 12 to 76 years of age, 41% male and 59% female, and 72% Caucasian and 28% non-Caucasian. Patients had persistent asthma and were not well controlled on medium dose of inhaled corticosteroids prior to randomization. All treatment groups were balanced with regard to baseline characteristics. Mean FEV1 and mean percent predicted FEV1 were similar among all treatment groups (2.33 L, 73%). Eight (4%) patients receiving DULERA 100 mcg/5 mcg, 13 (7%) patients receiving mometasone furoate 100 mcg, 47 (23%) patients receiving formoterol fumarate 5 mcg and 46 (23%) patients receiving placebo discontinued the study early due to treatment failure.

FEV1 AUC(0-12 hr) was assessed as a co-primary efficacy endpoint to evaluate the contribution of the formoterol component to DULERA. Patients receiving DULERA 100 mcg/5 mcg had significantly higher increases from baseline at Week 12 in mean FEV1 AUC(0-12 hr) compared to mometasone furoate 100 mcg (the primary treatment comparison) and vs. placebo (both p<0.001) (Figure 1). These differences were maintained through Week 26. Figure 1 shows the change from baseline post-dose serial FEV1 evaluations in Trial 1.

Figure 1:

Trial 1 - DULERA 100 mcg/5 mcg - FEV1 Serial Evaluations for Observed Cases at Week 12 Change from Baseline by Treatment

Clinically judged deteriorations in asthma or reductions in lung function were assessed as another primary endpoint to evaluate the contribution of mometasone furoate 100 mcg to DULERA 100 mcg/5 mcg (primary treatment comparison DULERA vs. formoterol). Deteriorations in asthma were defined as any of the following: a 20% decrease in FEV1; a 30% decrease in PEF on two or more consecutive days; emergency treatment, hospitalization, or treatment with systemic corticosteroids or other asthma medications not allowed per protocol. Fewer patients who received DULERA 100 mcg/5 mcg reported an event compared to patients who received formoterol 5 mcg (p<0.001).

Table 3: Trial 1 - Clinically Judged Deterioration in Asthma or Reduction in Lung Function [Includes only the first event day for each patient. Patients could have experienced more than one event criterion.]
 | DULERA 100 mcg/ 5 mcg [Two inhalations, twice daily.] (n=191) | Mometasone Furoate 100 mcg (n=192) | Formoterol 5 mcg (n=202) | Placebo (n=196)
Clinically judged deterioration in asthma or reduction in lung function | 58 (30%) | 65 (34%) | 109 (54%) | 109 (56%)
Decrease in FEV1 [Decrease in absolute FEV1 below the treatment period stability limit (defined as 80% of the average of the two predose FEV1 measurements taken 30 minutes and immediately prior to the first dose of randomized trial medication).] | 18 (9%) | 19 (10%) | 31 (15%) | 41 (21%)
Decrease in PEF [Decrease in AM or PM peak expiratory flow (PEF) on 2 or more consecutive days below the treatment period stability limit (defined as 70% of the AM or PM PEF obtained over the last 7 days of the run-in period).] | 37 (19%) | 41 (21%) | 62 (31%) | 61 (31%)
Emergency treatment | 0 | 1 (<1%) | 4 (2%) | 1 (<1%)
Hospitalization | 1 (<1%) | 0 | 0 | 0
Treatment with excluded asthma medication [Thirty patients received glucocorticosteroids; 1 patient received formoterol via dry powder inhaler in the Formoterol 5 mcg group.] | 2 (1%) | 4 (2%) | 17 (8%) | 8 (4%)

The change in mean trough FEV1 from baseline to Week 12 was assessed as another endpoint to evaluate the contribution of mometasone furoate 100 mcg to DULERA 100 mcg/5 mcg. A significantly greater increase in mean trough FEV1 was observed for DULERA 100 mcg/5 mcg compared to formoterol 5 mcg (the primary treatment comparison) as well as to placebo (Table 4).

Table 4: Trial 1 – Change in Trough FEV1 from Baseline to Week 12
Treatment Arm | N | Baseline (L) | Change From Baseline at Week 12 (L) | Treatment Difference from Placebo (L) | P-Value vs. Placebo | P-Value vs. Formoterol
DULERA 100 mcg/5 mcg | 167 | 2.33 | 0.13 | 0.18 | <0.001 | <0.001
Mometasone furoate 100 mcg | 175 | 2.36 | 0.07 | 0.12 | <0.001 | 0.058
Formoterol fumarate 5 mcg | 141 | 2.29 | 0.00 | 0.05 | 0.170
Placebo | 145 | 2.30 | -0.05
LS means and p-values are from Week 12 estimates of a longitudinal analysis model.

The effect of DULERA 100 mcg/5 mcg, two inhalations twice daily on selected secondary efficacy endpoints, including proportion of nights with nocturnal awakenings (-60% vs. -15%), change in total rescue medication use (-0.6 vs. +1.1 puffs/day), change in morning peak flow (+18.1 vs. -28.4 L/min) and evening peak flow (+10.8 vs. -32.1 L/min) further supports the efficacy of DULERA 100 mcg/5 mcg compared to placebo.

The subjective impact of asthma on patients' health-related quality of life was evaluated by the Asthma Quality of Life Questionnaire (AQLQ(S)) (based on a 7-point scale where 1 = maximum impairment and 7 = no impairment). A change from baseline ≥0.5 points is considered a clinically meaningful improvement. The mean difference in AQLQ between patients receiving DULERA 100 mcg/5 mcg and placebo was 0.5 [95% CI 0.32, 0.68].

Trial 2: Clinical Trial With DULERA 200 mcg/5 mcg

This 12-week double-blind trial (NCT00381485) evaluated 728 patients 12 years of age and older comparing DULERA 200 mcg/5 mcg (n=255 patients) with DULERA 100 mcg/5 mcg (n=233 patients) and mometasone furoate 200 mcg (n=240 patients), each administered as 2 inhalations twice daily by metered dose inhalation aerosols. All other maintenance therapies were discontinued. This trial included a 2 to 3-week run-in period with mometasone furoate 200 mcg, 2 inhalations twice daily. Patients had persistent asthma and were uncontrolled on high dose inhaled corticosteroids prior to study entry. All treatment groups were balanced with regard to baseline characteristics. This trial included patients ranging from 12 to 84 years of age, 44% male and 56% female, and 89% Caucasian and 11% non-Caucasian. Mean FEV1 and mean percent predicted FEV1 values were similar among all treatment groups (2.05 L, 66%). Eleven (5%) patients receiving DULERA 100 mcg/5 mcg, 8 (3%) patients receiving DULERA 200 mcg/5 mcg and 13 (5%) patients receiving mometasone furoate 200 mcg discontinued the trial early due to treatment failure.

The primary efficacy endpoint was the mean change in FEV1 AUC(0-12 hr) from baseline to Week 12. Patients receiving DULERA 100 mcg/5 mcg and DULERA 200 mcg/5 mcg had significantly greater increases from baseline at Day 1 in mean FEV1 AUC(0-12 hr) compared to mometasone furoate 200 mcg. The difference was maintained over 12 weeks of therapy.

Mean change in trough FEV1 from baseline to Week 12 was also assessed to evaluate the relative contribution of mometasone furoate to DULERA 100 mcg/5 mcg and DULERA 200 mcg/5 mcg (Table 5). A greater numerical increase in the mean trough FEV1 was observed for DULERA 200 mcg/5 mcg compared to DULERA 100 mcg/5 mcg and mometasone furoate 200 mcg.

Table 5: Trial 2 – Change in Trough FEV1 from Baseline to Week 12
Treatment Arm | N | Baseline (L) | Change from Baseline at Week 12 (L)
DULERA 100 mcg/5 mcg | 232 | 2.10 | 0.14
DULERA 200 mcg/5 mcg | 255 | 2.05 | 0.19
Mometasone furoate 200 mcg | 239 | 2.07 | 0.10

Clinically judged deterioration in asthma or reduction in lung function was assessed as an additional endpoint. Fewer patients who received DULERA 200 mcg/5 mcg or DULERA 100/5 mcg compared to mometasone furoate 200 mcg alone reported an event, defined as in Trial 1 by any of the following: a 20% decrease in FEV1; a 30% decrease in PEF on two or more consecutive days; emergency treatment, hospitalization, or treatment with systemic corticosteroids or other asthma medications not allowed per protocol.

Table 6: Trial 2 - Clinically Judged Deterioration in Asthma or Reduction in Lung Function [Includes only the first event day for each patient. Patients could have experienced more than one event criterion.]
 | DULERA 100 mcg/ 5 mcg [Two inhalations, twice daily.] (n=233) | DULERA 200 mcg/ 5 mcg (n=255) | Mometasone Furoate 200 mcg (n=240)
Clinically judged deterioration in asthma or reduction in lung function | 29 (12%) | 31 (12%) | 44 (18%)
Decrease in FEV1 [Decrease in absolute FEV1 below the treatment period stability limit (defined as 80% of the average of the two predose FEV1 measurements taken 30 minutes and immediately prior to the first dose of randomized trial medication).] | 23 (10%) | 17 (7%) | 33 (14%)
Decrease in PEF on two consecutive days [Decrease in AM or PM peak expiratory flow (PEF) below the treatment period stability limit (defined as 70% of the AM or PM PEF obtained over the last 7 days of the run-in period).] | 2 (1%) | 4 (2%) | 3 (1%)
Emergency treatment | 2 (1%) | 1 (<1%) | 1 (<1%)
Hospitalization | 0 | 1 (<1%) | 0
Treatment with excluded asthma medication [Twenty four patients received glucocorticosteroids; 1 patient received albuterol in the DULERA 200 mcg / 5 mcg group.] | 5 (2%) | 8 (3%) | 12 (5%)

Other Studies in Adults

In addition to Trial 1 and Trial 2, the safety and efficacy of the individual components, mometasone furoate MDI 100 mcg and 200 mcg (each administered as 2 inhalations by MDI), in comparison to placebo were demonstrated in two other, 12-week, placebo-controlled trials that evaluated the mean change in FEV1 from baseline as a primary endpoint. The safety and efficacy of formoterol MDI 5 mcg (administered as 2 inhalations twice daily) alone in comparison to placebo was replicated in another 26-week trial (NCT00383552) that also evaluated the same endpoint with a lower dose of mometasone furoate MDI in combination with formoterol.

Pediatric Patients Aged 5 to Less Than 12 Years

The efficacy of DULERA 50 mcg/5 mcg in children aged 5 to less than 12 years was demonstrated in a randomized, active-controlled, multicenter clinical trial (NCT02741271) in which DULERA 50 mcg/5 mcg (administered as two inhalations, twice daily; n=91) was compared with mometasone furoate MDI 50 mcg (administered as two inhalations, twice daily; n=90), in 181 asthma patients aged 5 to less than 12 years. These participants had been adequately controlled on an ICS/LABA for at least 4 weeks and had no symptoms of asthma worsening during a 2-week run-in on mometasone furoate MDI 50 mcg (administered as two inhalations twice daily). Primary endpoint results showed that patients receiving DULERA 50 mcg/5 mcg had a statistically significant change from baseline to Week 12 in 60-min AM post-dose % predicted FEV1 compared to mometasone furoate MDI 50 mcg (5.21, 95% CI: 3.22, 7.20) [Figure 2]. Bronchodilatory improvement with DULERA 50 mcg/5 mcg relative to mometasone furoate MDI 50 mcg was significant from the first assessment at 5 minutes and was sustained through 4 hours post-dose. These improvements were evident as early as the first dose and were maintained through Week 12.

Figure 2: Change from Baseline AM Post-Dose in % Predicted FEV1 Through Week 12

MF = mometasone furoate; MF/F = mometasone furoate/formoterol fumarate
Population consists of all subjects who received at least one dose of blinded treatment and completed at least one efficacy evaluation.
Treatment Effects were estimated using the Primary Analysis Method [i.e., a cLDA model with control-based multiple imputation, including terms for treatment, time, age strata (5-7 yrs., 8-11 yrs.), treatment by time interaction, and region (US, ex-US)].

Postmarketing Safety and Efficacy Trial with DULERA

This 26-week double-blind, randomized control trial evaluated 11,729 patients, 12 years of age and older, who received at least one dose of DULERA (100 mcg/5 mcg or 200 mcg/5 mcg, n=5868) or mometasone furoate monotherapy (100 mcg or 200 mcg, n=5861) each administered as 2 inhalations twice daily by metered dose inhalation aerosols (NCT01471340). The primary safety objective was to evaluate whether the addition of formoterol to mometasone furoate (DULERA) was non-inferior to mometasone furoate in risk of serious asthma-related events (adjudicated hospitalization, intubation, and death). A blinded adjudication committee determined whether events were asthma-related. The study was designed to rule out a pre-defined risk margin of 2.0. Enrolled patients had a diagnosis of persistent asthma, had been receiving a stable dose of asthma maintenance therapy for at least 4 weeks and had a history of one to four asthma exacerbations requiring hospitalization or systemic corticosteroid use in the previous year. The assigned dose level of inhaled corticosteroid was based on the patients' disease severity, considering their prior asthma medication and current level of asthma control. The study included patients ranging in age from 12 to 88 years (median age 47 years), and were 66% female and 77% Caucasian.

DULERA was non-inferior to mometasone furoate in terms of time to first serious asthma-related event based on the pre-specified risk margin with an estimated hazard ratio of 1.22 [95% CI: 0.76, 1.94].

Table 7: Serious Asthma-Related Event (Postmarketing Trial)
 | DULERA [Actual treatment used for analysis.] n (%) | Mometasone Furoate n (%) | Total n (%) | DULERA vs. Mometasone Furoate
Patients in population | 5868 | 5861 | 11,729 | Hazard Ratio [The hazard ratio for time to first event was based on a Cox proportional hazard model with covariates of treatment (DULERA vs. mometasone furoate) and inhaled corticosteroid dose level (100 mcg vs. 200 mcg), as treated.] (95% CI)
Serious Asthma-related Event [Results provided for all randomized patients who received at least one dose of DULERA (100 mcg/5 mcg and 200 mcg/5 mcg, two inhalations, prescribed twice daily) or mometasone furoate (100 mcg and 200 mcg, two inhalations, prescribed twice daily).] , [Number of patients with an event that occurred within 6 months after the first use of study drug or 7 days after the last date of study drug, whichever date was later. Patients can have one or more events, but only the first event was counted for analysis. A blinded adjudication committee determined whether events were asthma related.] | 39 (0.66) | 32 (0.55) | 71 (0.6) | 1.22 (0.76, 1.94)
Asthma-Related Hospitalization (≥24 hr stay) | 39 (0.66) | 32 (0.55) | 71 (0.6)
Asthma-Related Intubation (Endotracheal) | 0 | 0 | 0
Asthma-Related Death | 0 | 0 | 0

The key efficacy endpoint was time to first asthma exacerbation [defined as a clinical deterioration of asthma associated with systemic corticosteroid use for ≥3 consecutive days (or ≥1 depot injectable), emergency department visits <24 hours requiring systemic corticosteroid, or hospital stays of ≥24 hours]. The estimated hazard ratio for time to first exacerbation for DULERA relative to mometasone furoate was 0.89 [95% CI: 0.8, 0.98]. This outcome was primarily driven by a reduction in those events requiring systemic corticosteroid use, which accounted for 87% of the total number of first asthma exacerbations.

16 HOW SUPPLIED/STORAGE AND HANDLING

16.1 How Supplied

DULERA is available in three strengths and supplied in the following package sizes (Table 8):

Table 8
Package | NDC | Strength Identifier (Color Band) [Included on the outer carton, actuator, and canister labels.]
DULERA 50 mcg/5 mcg 120 inhalations | 78206-125-01 | Blue
DULERA 100 mcg/5 mcg 120 inhalations | 78206-127-01 | Yellow
DULERA 100 mcg/5 mcg 60 inhalations (institutional pack) | 78206-127-02 | Yellow
DULERA 200 mcg/5 mcg 120 inhalations | 78206-126-01 | Purple
DULERA 200 mcg/5 mcg 60 inhalations (institutional pack) | 78206-126-02 | Purple

Each strength is supplied as a pressurized aluminum canister that has a blue plastic actuator integrated with a dose counter and a green dust cap. Each 120-inhalation canister has a net fill weight of 13 grams and each 60-inhalation canister has a net fill weight of 8.8 grams. Each canister is placed into a carton. Each carton contains 1 canister and a Patient Information leaflet.

Initially the dose counter will display "64" or "124" actuations. After the initial priming with 4 actuations, the dose counter will read "60" or "120" and the inhaler is now ready for use.

16.2 Storage and Handling

Only use the DULERA canister with the DULERA actuator. Do not use the DULERA actuator with any other inhalation drug product. Do not use actuators from other products with the DULERA canister.

Do not remove the canister from the actuator because the correct amount of medication may not be discharged; the dose counter may not function properly; reinsertion may cause the dose counter to count down by 1 and discharge a puff.

The correct amount of medication in each inhalation cannot be ensured after the labeled number of actuations from the canister has been used, even though the inhaler may not feel completely empty and may continue to operate. Discard the inhaler when the labeled number of actuations has been used (the dose counter will read "0").

Store at controlled room temperature 20°C–25°C (68°F–77°F); excursions permitted to 15°C–30°C (59°F–86°F) [see USP Controlled Room Temperature].

After priming, store the inhaler with the mouthpiece down or in a horizontal position.

For best results, keep the canister at room temperature before use. Shake well and remove the cap from the mouthpiece of the actuator before using. Keep out of reach of children. Avoid spraying in eyes.

Contents Under Pressure: Do not puncture. Do not use or store near heat or open flame. Exposure to temperatures above 120°F may cause bursting. Never throw container into fire or incinerator.

17 PATIENT COUNSELING INFORMATION

Advise the patient to read the FDA-approved patient labeling (Patient Information and Instructions for Use).

Serious Asthma-Related Events

Inform patients with asthma that LABA when used alone increases the risk of asthma-related hospitalization, or asthma-related death. Available data show that when ICS and LABA are used together, such as with DULERA, there is not a significant increase in risk of these events.

Not for Acute Symptoms

DULERA is not indicated to relieve acute asthma symptoms and extra doses should not be used for that purpose. Treat acute symptoms with an inhaled, short-acting, beta2-agonist (the health care provider should prescribe the patient with such medication and instruct the patient in how it should be used).

Instruct patients to seek medical attention immediately if they experience any of the following:

- If their symptoms worsen
- Significant decrease in lung function as outlined by the physician
- If they need more inhalations of a short-acting beta2-agonist than usual

Advise patients not to increase the dose or frequency of DULERA. Do not exceed the daily dosage of DULERA of two inhalations twice daily. If they miss a dose, instruct patients to take their next dose at the same time they normally do. DULERA provides bronchodilation for up to 12 hours.

Instruct patients not to stop or reduce DULERA therapy without physician/provider guidance since symptoms may recur after discontinuation [see Warnings and Precautions (5.2)].

Do Not Use Additional Long-Acting Beta2-Agonists

When patients are prescribed DULERA, other long-acting beta2-agonists should not be used [see Warnings and Precautions (5.3)].

Risks Associated With Corticosteroid Therapy

Local Effects: Advise patients that localized infections with Candida albicans occurred in the mouth and pharynx in some patients. If oropharyngeal candidiasis develops, treat with appropriate local or systemic (i.e., oral) antifungal therapy while still continuing with DULERA therapy, but at times therapy with DULERA may need to be temporarily interrupted under close medical supervision. Rinsing the mouth after inhalation is advised [see Warnings and Precautions (5.4)].

Immunosuppression: Warn patients who are on immunosuppressant doses of corticosteroids to avoid exposure to chickenpox or measles and, if exposed, to consult their physician without delay. Inform patients of potential worsening of existing tuberculosis, fungal, bacterial, viral, or parasitic infections, or ocular herpes simplex [see Warnings and Precautions (5.5)].

Hypercorticism and Adrenal Suppression: Advise patients that DULERA may cause systemic corticosteroid effects of hypercorticism and adrenal suppression. Additionally, instruct patients that deaths due to adrenal insufficiency have occurred during and after transfer from systemic corticosteroids. Instruct patients to taper slowly from systemic corticosteroids if transferring to DULERA [see Warnings and Precautions (5.7)].

Reduction in Bone Mineral Density: Advise patients who are at an increased risk for decreased BMD that the use of corticosteroids may pose an additional risk and that they should be monitored and, where appropriate, be treated for this condition [see Warnings and Precautions (5.12)].

Reduced Growth Velocity: Inform patients that orally inhaled corticosteroids, a component of DULERA, may cause a reduction in growth velocity when administered to pediatric patients. Physicians should closely follow the growth of pediatric patients taking corticosteroids by any route [see Warnings and Precautions (5.13)].

Glaucoma and Cataracts: Long-term use of inhaled corticosteroids may increase the risk of some eye problems (glaucoma or cataracts); consider regular eye examinations [see Warnings and Precautions (5.14)].

Risks Associated With Beta-Agonist Therapy

Inform patients that treatment with beta2-agonists may lead to adverse events which include palpitations, chest pain, rapid heart rate, tremor or nervousness [see Warnings and Precautions (5.11)].

Instructions for Use

Instruct patients regarding the following:

- Read the Patient Information before use and follow the Instructions for Use carefully.
- Remind patients to:
  - Remove the cap from the mouthpiece of the actuator before use.
  - After dosing, rinse their mouth with water without swallowing and spit out after breathing in the medicine. This will help reduce the risk of oropharyngeal candidiasis.
  - Not remove the canister from the actuator.
  - Not wash inhaler in water. The mouthpiece should be cleaned using a dry wipe after every 7 days of use.

Manufactured for: Organon LLC, a subsidiary of
ORGANON & Co.,
Jersey City, NJ 07302, USA

Manufactured by: Kindeva Drug Delivery Limited, Loughborough, United Kingdom.

For patent information: www.organon.com/our-solutions/patent/

The trademarks depicted herein are owned by their respective companies.

© 2025 Organon group of companies. All rights reserved.

uspi-og0887a-ao-2506r001

PATIENT INFORMATION
DULERA® [dew-LAIR-ah] 50 mcg/5 mcg
(mometasone furoate 50 mcg and formoterol fumarate dihydrate 5 mcg)
Inhalation Aerosol
DULERA® 100 mcg/5 mcg
(mometasone furoate 100 mcg and formoterol fumarate dihydrate 5 mcg)
Inhalation Aerosol
DULERA® 200 mcg/5 mcg
(mometasone furoate 200 mcg and formoterol fumarate dihydrate 5 mcg)
Inhalation Aerosol

Read the Patient Information leaflet that comes with DULERA® before you start using it and each time you get a refill. There may be new information. The Patient Information leaflet does not take the place of talking to your healthcare provider about your medical condition or treatment.

What is DULERA?

- DULERA combines an inhaled corticosteroid medicine (ICS), mometasone furoate, and a long-acting beta2-agonist medicine (LABA), formoterol.
- ICS medicines such as mometasone furoate help to decrease inflammation in the lungs. Inflammation in the lungs can lead to breathing problems.
- LABA medicines such as formoterol help the muscles around the airways in your lungs stay relaxed to prevent asthma symptoms, such as wheezing, cough, chest tightness, and shortness of breath. These symptoms can happen when the muscles around the airways tighten. This makes it hard to breathe.
- DULERA is not used to relieve sudden breathing problems and will not replace a rescue inhaler.
- It is not known if DULERA is safe and effective in children less than 5 years of age.
- DULERA is used for asthma as follows:
  - DULERA is a prescription medicine used to control symptoms of asthma and prevent symptoms such as wheezing in people 5 years of age and older.
  - DULERA contains formoterol. LABA medicines such as formoterol when used alone increase the risk of hospitalizations and death from asthma problems. DULERA contains an ICS and a LABA. When an ICS and LABA are used together, there is not a significant increased risk in hospitalizations and death from asthma problems.
  - DULERA is not for adults and children with asthma who are well controlled with an asthma control medicine, such as a low to medium dose ICS medicine. DULERA is for adults and children with asthma who need both an ICS and LABA medicine.

Do not use DULERA:

- to treat sudden severe symptoms of asthma.
- as a rescue inhaler.
- if you are allergic to any of the ingredients in DULERA. See the end of this Patient Information leaflet for a list of ingredients in DULERA.

Before and during treatment with DULERA, tell your healthcare provider about all of your medical conditions, including if you:

- have heart problems.
- have high blood pressure.
- have seizures.
- have thyroid problems.
- have diabetes.
- have liver problems.
- have osteoporosis.
- have an immune system problem.
- have eye problems such as increased pressure in the eye, glaucoma, cataracts, blurred vision, or other changes in your vision.
- are allergic to any medicines.
- are exposed to chickenpox or measles.
- have an aneurysm (swelling of an artery).
- have a pheochromocytoma (a tumor of the adrenal gland that can affect your blood pressure).
- are scheduled to have surgery.
- are pregnant or planning to become pregnant. It is not known if DULERA may harm your unborn baby.
- are breastfeeding. It is not known if DULERA passes into your milk and if it can harm your baby. You and your healthcare provider should decide if you will take DULERA while breastfeeding.

Tell your healthcare provider about all the medicines you take including prescription and over-the-counter medicines, vitamins, and herbal supplements. DULERA and certain other medicines may interact with each other. This may cause serious side effects.
Especially, tell your healthcare provider if you take antifungal medicines, such as ketoconazole, or anti-HIV medicines, such as ritonavir and cobicistat-containing products. The anti-HIV medicines NORVIR® (ritonavir capsules) Soft Gelatin, NORVIR® (ritonavir oral solution), and KALETRA® (lopinavir/ritonavir) Tablets contain ritonavir.
For some medicines (including medicines for HIV such as ritonavir, cobicistat-containing products, and certain antifungals and antibiotics) your doctor may wish to monitor you carefully.
Know the medicines you take. Keep a list and show it to your healthcare provider and pharmacist each time you get a new medicine.

How should I use DULERA?
See the step-by-step instructions for using DULERA at the end of this Patient Information leaflet. Do not use DULERA unless your healthcare provider has taught you and you understand how to use it. Ask your healthcare provider or pharmacist if you have any questions.

- Use DULERA exactly as prescribed. Do not use DULERA more often than prescribed. DULERA comes in 3 strengths. Your healthcare provider has prescribed the strength that is best for you. Note the differences between DULERA and your other inhaled medicines, including the differences in prescribed use and physical appearance.
- For children aged 5 to less than 12 years, use DULERA 50 mcg/5 mcg.
- For adults and adolescents 12 years of age and older, use DULERA 100 mcg/5 mcg or DULERA 200 mcg/5 mcg.
- DULERA should be taken every day as 2 puffs in the morning and 2 puffs in the evening.
- If you miss a dose of DULERA, skip your missed dose and take your next dose at your regular time. Do not take DULERA more often or use more puffs than you have been prescribed.
- While you are using DULERA 2 times each day, do not use other medicines that contain a long-acting beta2-agonist (LABA) for any reason. Ask your healthcare provider or pharmacist if any of your other medicines are LABA medicines.
- If you take more DULERA than your healthcare provider has prescribed, get medical help right away if you have any unusual symptoms, such as problems breathing, palpitations, chest pain, increased heart rate, nervousness or shakiness.
- Do not change or stop using DULERA or other asthma medicines used to control or treat your breathing problems unless told to do so by your healthcare provider. Your healthcare provider will change your medicines as needed.
- DULERA does not relieve sudden asthma symptoms. Always have a rescue inhaler with you to treat sudden symptoms. Use your rescue inhaler if you have breathing problems between doses of DULERA. If you do not have a rescue inhaler, call your healthcare provider to have one prescribed for you.
- Remove the cap from the mouthpiece of the actuator before using DULERA.
- Do not remove the canister from the actuator because:
  - You may not receive the correct amount of medicine.
  - The dose counter may not function properly.
  - Reinsertion may cause the dose counter to count down by 1 and may discharge a puff.
- After each dose (2 puffs) of DULERA, rinse your mouth with water. Spit out the water. Do not swallow it. This will help to lessen the chance of getting a yeast infection (thrush) in the mouth and throat.
- Prime (sprays released into the air before use) your inhaler away from your face. Do not spray DULERA in your eyes. If you accidentally get DULERA in your eyes, rinse your eyes with water and if redness or irritation continues, call your healthcare provider.
- Call your healthcare provider or get medical care right away if:
  - your breathing problems worsen with DULERA
  - you need to use your rescue inhaler more often than usual
  - your rescue inhaler does not work as well for you at relieving symptoms
  - you need to use 4 or more inhalations of your rescue inhaler for 2 or more days in a row
  - you use 1 whole canister of your rescue inhaler in 4 weeks' time
  - your peak flow meter results decrease. Your healthcare provider will tell you the numbers that are right for you
  - your asthma symptoms do not improve after using DULERA regularly for 2 weeks

What are the possible side effects of DULERA?
DULERA may cause serious side effects, including:

- Thrush in the mouth and throat. You may develop thrush, a yeast infection (Candida albicans), in your mouth or throat. After each dose of DULERA (2 puffs), rinse your mouth with water. Spit out the water. Do not swallow it. This will help to prevent thrush in your mouth or throat.
- Immune system effects and a higher chance for infections. Signs of infection may include:

- fever
- nausea
- chills

- feeling tired
- body aches

- pain
- vomiting

- Adrenal insufficiency. Adrenal insufficiency is a condition in which the adrenal glands do not make enough steroid hormones. This can happen when you stop taking oral corticosteroid medicines and start inhaled corticosteroid medicines.
- Increased wheezing right after taking DULERA. Always have a rescue inhaler with you to treat sudden wheezing.
- Serious allergic reactions. Call your healthcare provider or get emergency medical care if you get any of the following symptoms of a serious allergic reaction:

- rash
- swelling, including swelling of the face, mouth, and tongue

- hives
- breathing problems

- Using too much of a LABA medicine may cause:

- chest pain
- a fast and irregular heartbeat
- tremor
- dizziness
- seizures

- increased or decreased blood pressure
- headache
- nervousness
- weakness
- electrocardiogram (ECG) changes

- Lower bone mineral density. This may be a problem for people who already have a higher chance for low bone density (osteoporosis).
- Slowed growth in children. A child's growth should be checked often.
- Eye problems including glaucoma, cataracts, and blurred vision. You should have regular eye exams while using DULERA.
- Decreases in blood potassium levels (hypokalemia).
- Increases in blood sugar levels (hyperglycemia).

The most common side effects reported while using DULERA include:

- inflammation of the nose and throat (nasopharyngitis)
- inflammation of the sinuses (sinusitis)
- headache
- flu
- upper respiratory infection

Tell your healthcare provider about any side effect that bothers you or that does not go away.
These are not all the side effects of DULERA. Ask your healthcare provider or pharmacist for more information.
Call your doctor for medical advice about side effects. You may report side effects to FDA at 1-800-FDA-1088.
You may also report side effects to Organon LLC., a subsidiary of Organon & Co., at 1-844-674-3200.

How should I store DULERA?

- Store DULERA at room temperature between 68°F to 77°F (20°C to 25°C).
- After priming, store the inhaler with the mouthpiece down or sideways.
- The contents of your DULERA are under pressure. Do not puncture. Do not use or store near heat or open flame. Storage above 120°F may cause the canister to burst.
- Do not throw container into fire or incinerator.
- Keep DULERA and all medicines out of the reach of children.

General Information about the safe and effective use of DULERA.
Medicines are sometimes prescribed for purposes other than those listed in the Patient Information leaflet. Do not use DULERA for a condition for which it was not prescribed. Do not give your DULERA to other people, even if they have the same condition. It may harm them.
You can ask your healthcare provider or pharmacist for information about DULERA that was written for healthcare professionals.

What are the ingredients in DULERA?
Active ingredients: mometasone furoate and formoterol fumarate dihydrate
Inactive ingredients: hydrofluoroalkane (HFA-227), anhydrous alcohol and oleic acid

For more information about DULERA:
Go to www.DULERA.com or call 1-844-674-3200.

This Patient Information has been approved by the U.S. Food and Drug Administration

Revised: 6/2025

Patient Instructions for Use

DULERA®
DULERA® 50 mcg/5 mcg
(mometasone furoate 50 mcg and formoterol fumarate dihydrate 5 mcg) Inhalation Aerosol
DULERA® 100 mcg/5 mcg
(mometasone furoate 100 mcg and formoterol fumarate dihydrate 5 mcg) Inhalation Aerosol
DULERA® 200 mcg/5 mcg
(mometasone furoate 200 mcg and formoterol fumarate dihydrate 5 mcg) Inhalation Aerosol

How to use your DULERA

Before using your DULERA, read the complete instructions and use only as directed.

The parts of your DULERA:

There are 2 main parts to your DULERA inhaler – the metal canister that holds the medicine and the blue plastic actuator that sprays the medicine from the canister. The inhaler also has a green cap that covers the mouthpiece of the actuator (see Figure 1). The cap from the mouthpiece must be removed before use. The inhaler contains 60 or 120 actuations (puffs).

Figure 1

The inhaler comes with dose counter located on the plastic actuator. See Figure 1. The counter display will show the number of actuations (puffs) of medicine remaining. The dose counter will initially display "64" or "124" actuations remaining. Each time you press the canister, a puff of medicine is released and the counter will count down by 1. The counter will stop counting at 0.

- YOU SHOULD NOT REMOVE THE CANISTER FROM THE ACTUATOR because:
  - You may not receive the correct amount of medication.
  - The dose counter may not function properly.
  - Reinsertion may cause the counter to count down by 1 and may discharge a puff.
- Use the DULERA canister only with the actuator supplied with the product. Do not use parts of the DULERA inhaler with parts from any other inhalation medicine.

Before using your DULERA:

Note: Adults may assist children with using DULERA as prescribed. Children may use DULERA with or without a spacer device.

REMOVE THE CAP FROM THE MOUTHPIECE OF THE ACTUATOR (see Figure 2). Check the mouthpiece for objects before use. Make sure the canister is fully inserted into the actuator.

Figure 2

Priming your DULERA Inhaler:

Before you use DULERA for the first time, you must prime the inhaler.

1. To prime the inhaler, hold it in the upright position and release 4 actuations (puffs) into the air, away from your face.
2. Shake the inhaler well before each of the priming actuations. After priming 4 times, the dose counter should read either "60" or "120".
3. If you do not use your DULERA for more than 5 days, you will need to prime it again before use.

Using your DULERA

4. Confirm that the strength indicated on the actuator and canister labels matches the prescribed dosage.
5. REMOVE THE CAP FROM THE MOUTHPIECE OF THE ACTUATOR (see Figure 3). Check the mouthpiece for objects before use. Make sure the canister is fully inserted into the actuator.
6. Shake the inhaler well before each use.
7. Breathe out as fully as you comfortably can through your mouth. Push out as much air from your lungs as possible. Hold the inhaler in the upright position and place the mouthpiece into your mouth (see Figure 4). Close your lips around the mouthpiece.

Figure 3

Figure 4

8. Take a deep breath (inhale) in slowly through your mouth. While doing this, press down firmly and fully on the top of the canister until it stops moving in the actuator. Take your finger off the canister.
9. When you have finished breathing in, hold your breath as long as you comfortably can, up to 10 seconds. Then remove the inhaler from your mouth and breathe out through your nose, while keeping your lips closed.
10. Wait at least 30 seconds to take your second puff of DULERA.
11. Shake the inhaler well again and repeat steps 6 through 8 to take your second puff of DULERA.

After using your DULERA inhaler:

12. Replace the cap over the mouthpiece right away after use (see Figure 5).
  Figure 5
13. After you finish taking DULERA (2 puffs), rinse your mouth with water. Spit out the water. Do not swallow it.

Reading the counter

- The dose counter identifies the number of inhalations (puffs) left in your inhaler.
- The counter will count down each time you release a puff of medicine (either when preparing your DULERA inhaler for use or when taking the medicine).

When to replace your DULERA:

- It is important that you pay attention to the number of inhalations (puffs) left in your DULERA inhaler by reading the counter.
- When the counter reads 20, you should refill your prescription or ask your healthcare provider if you need a new prescription for DULERA.
- Throw away DULERA after the counter reaches 0, indicating that you have used the number of actuations on the product label and box. Your inhaler may not feel empty and it may continue to operate, but you will not get the right amount of medicine if you keep using it.
- Never try to change the numbers on the counter or remove the counter from the actuator.
- Do not use the inhaler after the expiration date.

How should I store DULERA?

- Store DULERA at room temperature between 68°F to 77°F (20°C to 25°C).
- After priming, store the inhaler with the mouthpiece down or sideways.
- The contents of your DULERA canister are under pressure. Do not puncture or throw the canister into a fire or incinerator. Do not use or store it near heat or open flame. Storage above 120ºF (50°C) may cause the canister to burst.
- Keep DULERA and all medicines out of the reach of children.

How to clean your DULERA:

The mouthpiece should be cleaned using a dry wipe after every 7 days of use.

Routine cleaning instructions:

- Remove the cap off the mouthpiece. Wipe the inside and outside surfaces of the actuator mouthpiece with a clean, dry, lint-free tissue or cloth. Do not wash or put any parts of your inhaler in water. Put the cap back on the mouthpiece after cleaning.
- Do not remove the canister from the actuator.
- Do not attempt to unblock the actuator with a sharp object, such as a pin.

Manufactured for: Organon LLC, a subsidiary of
ORGANON & Co.,
Jersey City, NJ 07302, USA

Manufactured by: Kindeva Drug Delivery Limited, Loughborough, United Kingdom.

This Instructions for Use has been approved by the U.S. Food and Drug Administration.

For patent information: www.organon.com/our-solutions/patent/

The trademarks depicted herein are owned by their respective companies.

© 2025 Organon group of companies. All rights reserved.

Revised: 6/2025

usppi-og0887a-ao-2506r001

PACKAGE LABEL

PRINCIPAL DISPLAY PANEL - 100 mcg/5 mcg Canister Carton

NDC 78206-127-01

Dulera®
(mometasone furoate and
formoterol fumarate dihydrate)
Inhalation Aerosol

100 mcg/5 mcg
per actuation

For oral inhalation only

SHAKE WELL BEFORE USING.

Dulera canister to be used with Dulera actuator only.

Rx only

120 Metered Actuations
Net Wt. 13g

PACKAGE LABEL

PRINCIPAL DISPLAY PANEL - 200 mcg/5 mcg Canister Carton

NDC 78206-126-01

Dulera®
(mometasone furoate and
formoterol fumarate dihydrate)
Inhalation Aerosol

200 mcg/5 mcg
per actuation

For oral inhalation only

SHAKE WELL BEFORE USING.

Dulera canister to be used with Dulera actuator only.

Rx only

120 Metered Actuations
Net Wt. 13g

PRINCIPAL DISPLAY PANEL - 50 mcg/5 mcg Canister Carton

NDC 78206-125-01

Dulera®
(mometasone furoate and
formoterol fumarate dihydrate)
Inhalation Aerosol

50 mcg/5 mcg
per actuation

For oral inhalation only

SHAKE WELL BEFORE USING.

Dulera canister to be used with Dulera actuator only.

Rx only

120 Metered Actuations
Net Wt. 13g